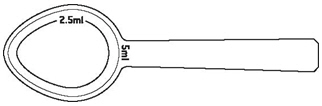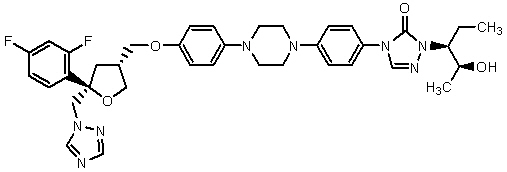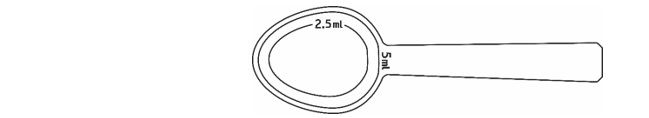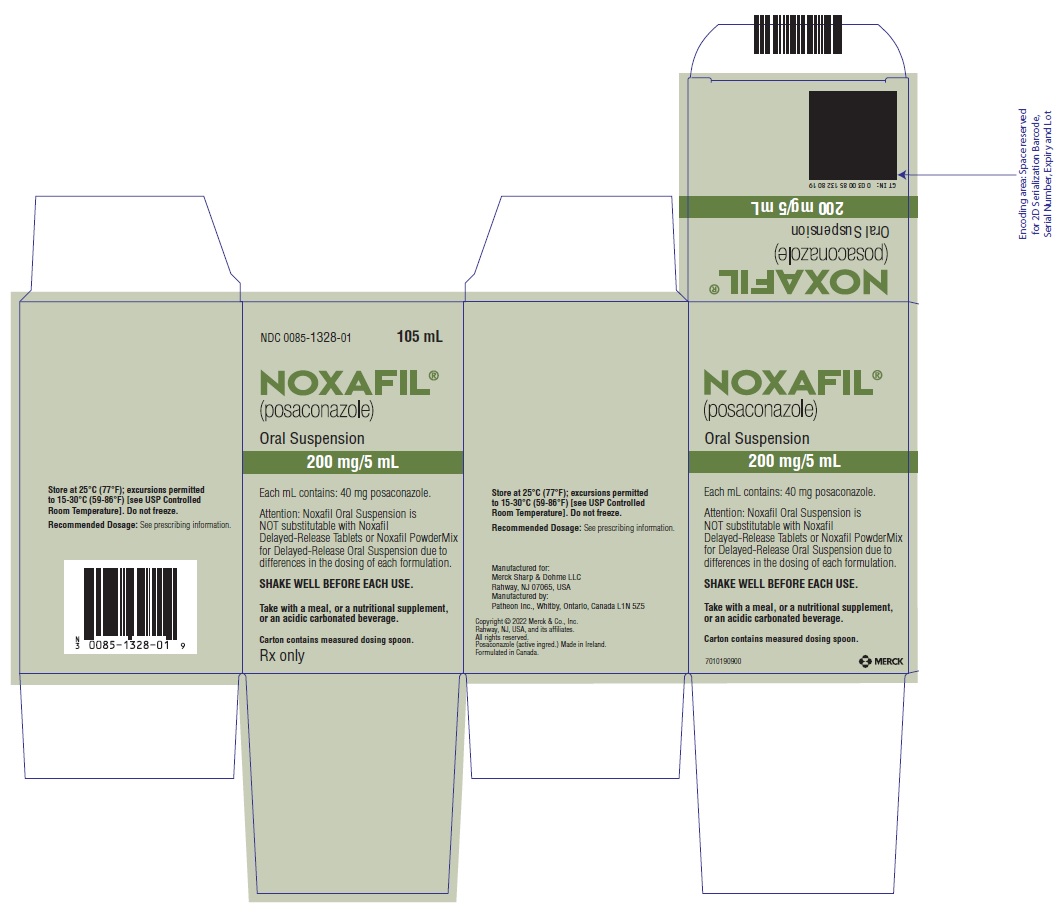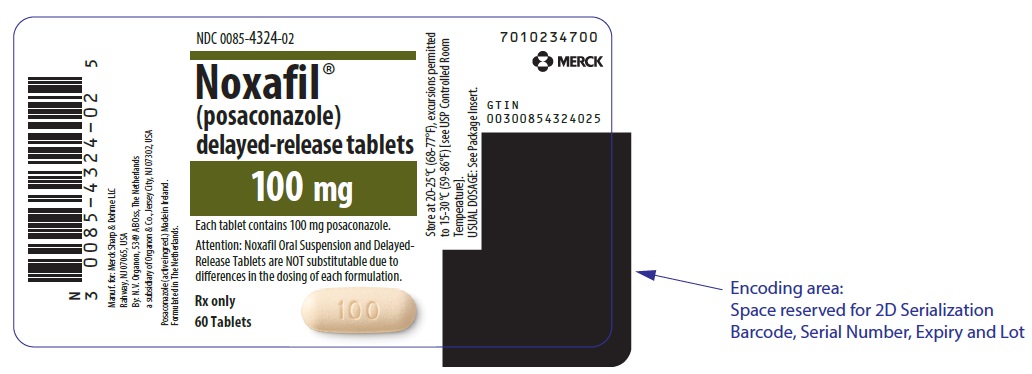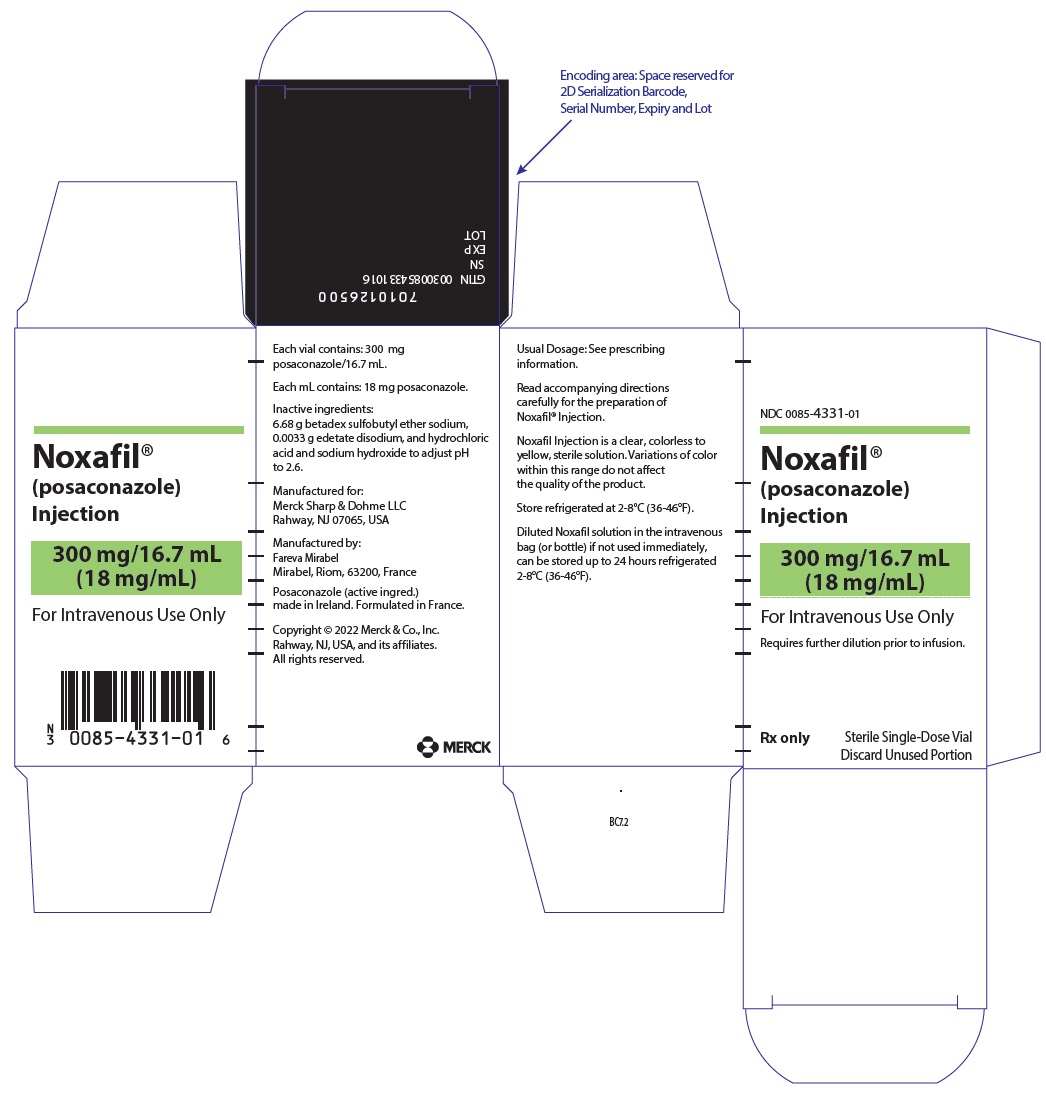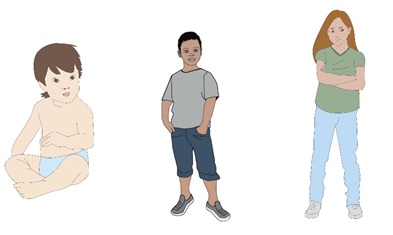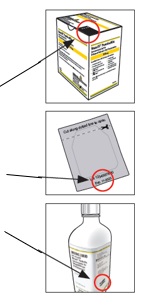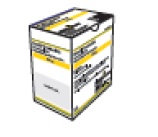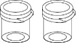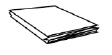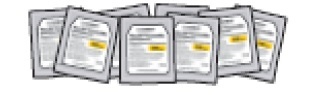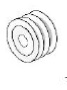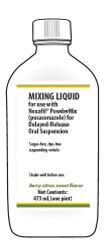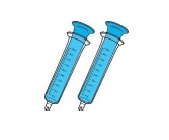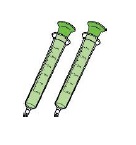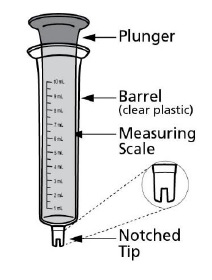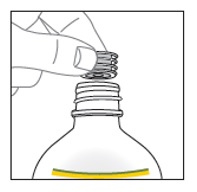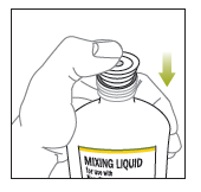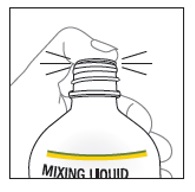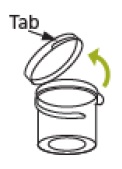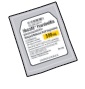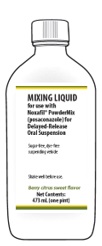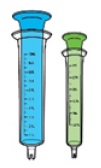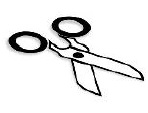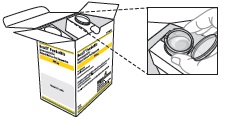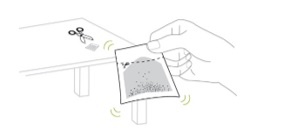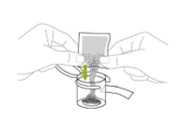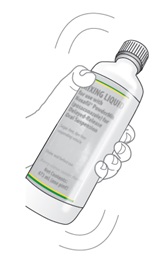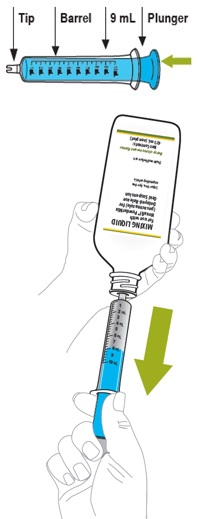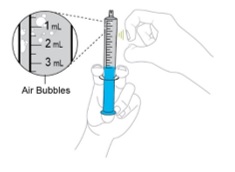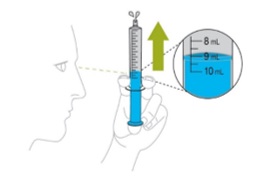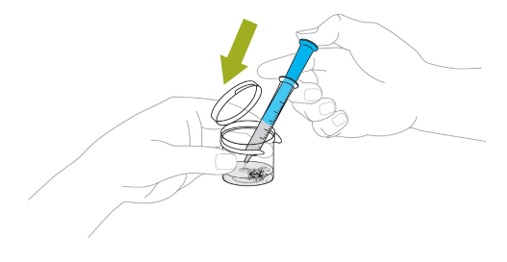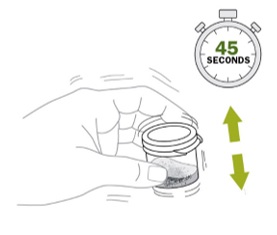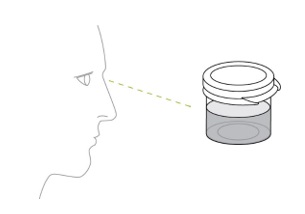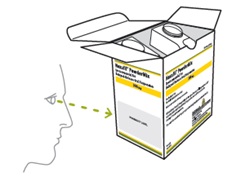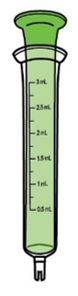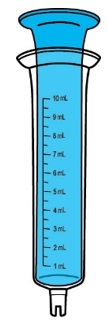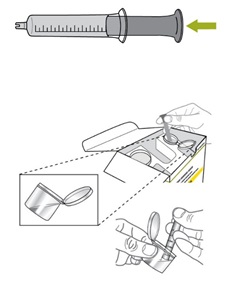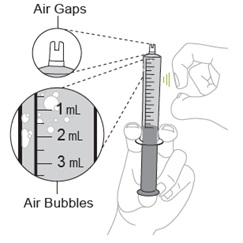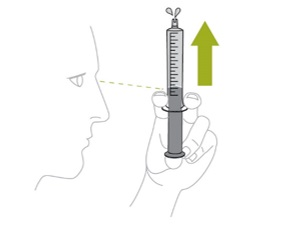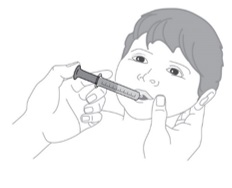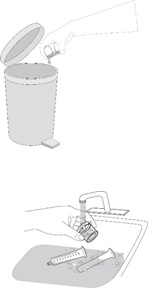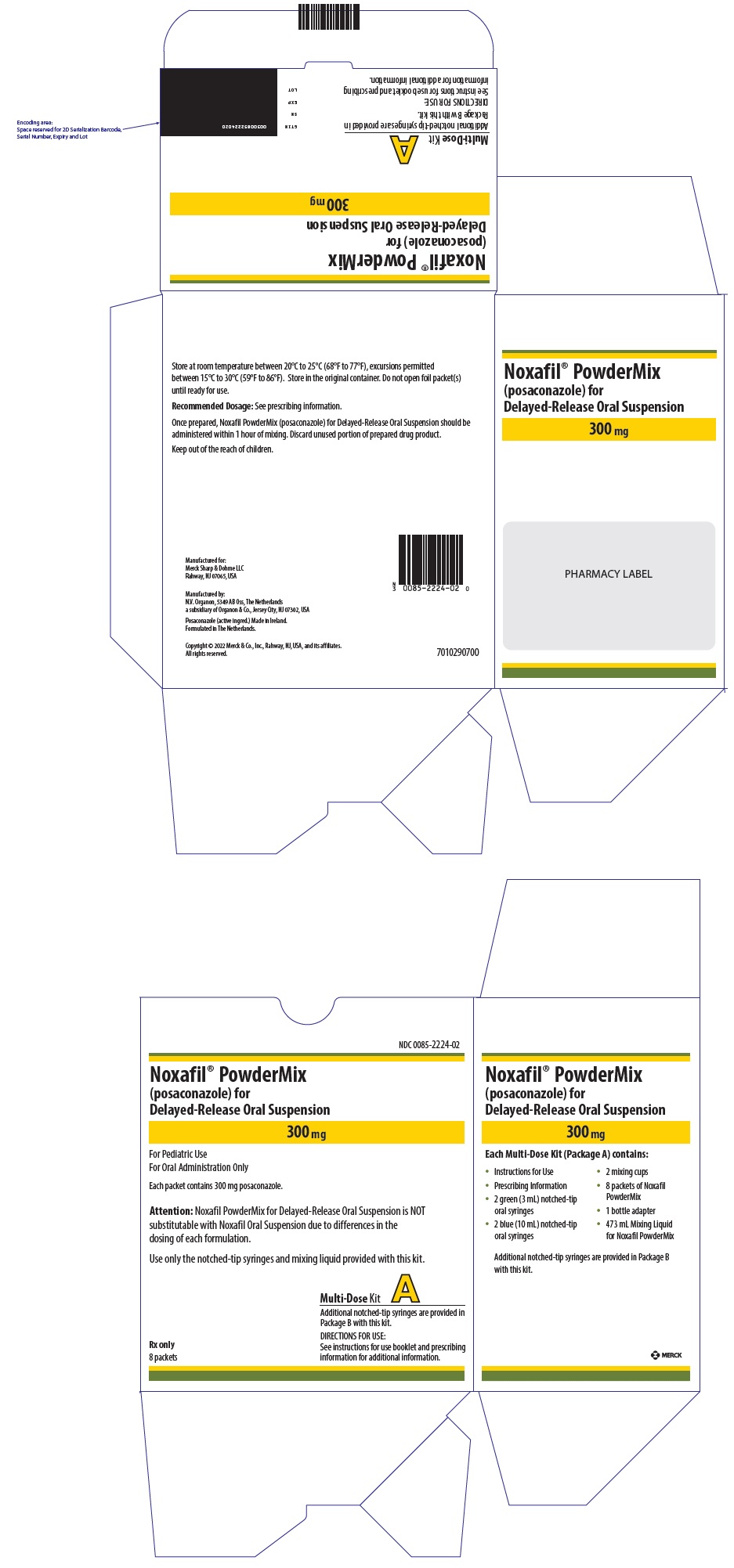 DRUG LABEL: NOXAFIL
NDC: 0085-1328 | Form: SUSPENSION
Manufacturer: Merck Sharp & Dohme LLC
Category: prescription | Type: HUMAN PRESCRIPTION DRUG LABEL
Date: 20260127

ACTIVE INGREDIENTS: posaconazole 40 mg/1 mL
INACTIVE INGREDIENTS: polysorbate 80; sodium benzoate; trisodium citrate dihydrate; citric acid monohydrate; glycerin; xanthan gum; anhydrous dextrose; titanium dioxide; water

HIGHLIGHTS OF PRESCRIBING INFORMATION

These highlights do not include all the information needed to use NOXAFIL safely and effectively. See full prescribing information for NOXAFIL.
NOXAFIL® (posaconazole) injection, for intravenous use
NOXAFIL® (posaconazole) delayed-release tablets, for oral use
NOXAFIL® (posaconazole) oral suspension
NOXAFIL® POWDERMIX (posaconazole) for delayed-release oral suspension
Initial U.S. Approval: 2006

RECENT MAJOR CHANGES

Indications and Usage (1.1, 1.2) | 1/2026
Dosage and Administration (2) | 1/2026

1 INDICATIONS AND USAGE

Noxafil is an azole antifungal indicated as follows:

- Noxafil is indicated for the treatment of invasive aspergillosis as follows: (1.1)
  - Noxafil injection: adults and pediatric patients 2 years of age and older who weigh 10 kg or greater
  - Noxafil delayed-release tablets: adults and pediatric patients 2 years of age and older who weigh greater than 40 kg
  - Noxafil PowderMix for delayed-release oral suspension: pediatric patients 2 years of age and older who weigh 10 kg to 40 kg
- Noxafil is indicated for the prophylaxis of invasive Aspergillus and Candida infections in patients who are at high risk of developing these infections due to being severely immunocompromised, such as hematopoietic stem cell transplant (HSCT) recipients with graft-versus-host disease (GVHD) or those with hematologic malignancies with prolonged neutropenia from chemotherapy as follows: (1.2)
  - Noxafil injection: adults and pediatric patients 2 years of age and older who weigh 10 kg or greater.
  - Noxafil delayed-release tablets: adults and pediatric patients 2 years of age and older who weigh greater than 40 kg
  - Noxafil oral suspension: adults and pediatric patients 13 years of age and older
  - Noxafil PowderMix for delayed-release oral suspension: pediatric patients 2 years of age and older who weigh 10 kg to 40 kg

- Noxafil oral suspension is indicated for the treatment of oropharyngeal candidiasis (OPC), including OPC refractory (rOPC) to itraconazole and/or fluconazole in adults and pediatric patients 13 years of age and older (1.3)

2 DOSAGE AND ADMINISTRATION

- Noxafil formulations are supplied in different dose strengths of posaconazole, are approved for different indications, age groups, and weights, have different dosages and duration of therapy; and have different preparation and administration instructions. (2.1)
- Noxafil oral suspension is not substitutable with Noxafil delayed-release tablets or Noxafil PowderMix for delayed-release oral suspension due to the differences in the dosing of each formulation. Therefore, follow the specific dosage recommendations for each of the formulations. (2.1, 2.2, 2.3)
- Noxafil injection must be administered through an in-line filter. (2.6)
- Administer Noxafil injection by intravenous infusion over approximately 90 minutes via a central venous line. (2.1, 2.6)
- Do NOT administer Noxafil injection as an intravenous bolus injection. (2.1)
- Administer Noxafil delayed-release tablets with or without food. (2.1)
- Administer Noxafil oral suspension with a full meal. (2.1)
- Administer Noxafil PowderMix for delayed-release oral suspension with food. (2.1)
- Administer Noxafil PowderMix for delayed-release oral suspension with the provided notched tip syringes only. (2.1)
- See the full prescribing information for important administration instructions and preparation instructions for Noxafil (injection, delayed-release tablets, and oral suspension) and Noxafil PowderMix delayed-release oral suspension (2.5, 2.6, 2.7, 2.8, 2.9, 2.10)

- For adult and pediatric patients aged 2 years of age and older, see the Full Prescribing Information for dosing recommendations for Noxafil injection, Noxafil delayed-release tablets, Noxafil oral suspension, and/or Noxafil PowderMix for delayed-release oral suspension based on the indication, age, and weight associated with the dosage form (1.1, 1.2, 1.3, 2.1, 2.2, 2.3, 2.4)

3 DOSAGE FORMS AND STRENGTHS

- Noxafil injection: 300 mg per vial (18 mg per mL) in a single-dose vial (3)
- Noxafil delayed-release tablet: 100 mg (3)
- Noxafil oral suspension: 40 mg per mL (3)
- Noxafil PowderMix for delayed-release oral suspension: 300 mg (3)

4 CONTRAINDICATIONS

- Known hypersensitivity to posaconazole or other azole antifungal agents. (4.1)
- Coadministration of Noxafil with the following drugs is contraindicated; Noxafil increases concentrations and toxicities of:
  - Sirolimus (4.2, 7.2)
  - CYP3A4 substrates (pimozide, quinidine): can result in QTc interval prolongation and cases of torsades de pointes (TdP) (4.3, 5.2, 7.2)
  - HMG-CoA Reductase Inhibitors Primarily Metabolized through CYP3A4 (4.4, 7.2)
  - Ergot alkaloids (4.5, 7.2)
  - Venetoclax: In patients with chronic lymphocytic leukemia (CLL) or small lymphocytic lymphoma (SLL) at initiation and during the ramp-up phase (4.6, 5.11, 7.2)
- Noxafil PowderMix for delayed-release oral suspension is contraindicated in patients with known or suspected Hereditary Fructose Intolerance (HFI). (4.7, 5.9, 8.4)

5 WARNINGS AND PRECAUTIONS

- Calcineurin-Inhibitor Toxicity: Noxafil increases concentrations of cyclosporine or tacrolimus; reduce dose of cyclosporine and tacrolimus and monitor concentrations frequently. (5.1)
- Arrhythmias and QTc Prolongation: Noxafil has been shown to prolong the QTc interval and cause cases of TdP. Administer with caution to patients with potentially proarrhythmic conditions. Do not administer with drugs known to prolong QTc interval and metabolized through CYP3A4. (5.2, 7.2)
- Electrolyte Disturbances: Monitor and correct, especially those involving potassium (K^+), magnesium (Mg^++), and calcium (Ca^++), before and during Noxafil therapy. (5.3)
- Pseudoaldosteronism: Manifested by the onset or worsening of hypertension, and abnormal laboratory findings. Monitor blood pressure and potassium levels, and manage as necessary. (5.4)
- Hepatic Toxicity: Elevations in liver tests may occur. Discontinuation should be considered in patients who develop abnormal liver tests or monitor liver tests during treatment. (5.5)
- Renal Impairment: Noxafil injection should be avoided in patients with moderate or severe renal impairment (eGFR less than 50 mL/min/1.73 m^2), unless an assessment of the benefit/risk to the patient justifies the use of Noxafil injection. (5.6, 8.6)
- Concomitant Use with Midazolam: Noxafil can prolong hypnotic/sedative effects. Monitor patients and benzodiazepine receptor antagonists should be available. (5.7, 7.2)
- Vincristine Toxicity: Concomitant administration of azole antifungals, including Noxafil, with vincristine has been associated with neurotoxicity and other serious adverse reactions; reserve azole antifungals, including Noxafil, for patients receiving a vinca alkaloid, including vincristine, who have no alternative antifungal treatment options. (5.8, 7.2)
- Risk in Patients with Hereditary Fructose Intolerance (HFI): Noxafil PowderMix for delayed-release oral suspension contains sorbitol. Risk of metabolic crisis with life-threatening hypoglycemia, hypophosphatemia, lactic acidosis, and hepatic failure. Obtain history of HFI symptoms in pediatric patients before Noxafil PowderMix for delayed-release oral suspension administration. (5.9, 8.4)
- Breakthrough Fungal Infections: Monitor patients with severe diarrhea or vomiting when receiving Noxafil delayed-release tablets, Noxafil oral suspension, and Noxafil PowderMix for delayed-release oral suspension. (5.10)
- Venetoclax Toxicity: Concomitant administration of Noxafil with venetoclax may increase venetoclax toxicities, including the risk of tumor lysis syndrome, neutropenia, and serious infections; monitor for toxicity and reduce venetoclax dose. (4.6, 5.11, 7.2)

6 ADVERSE REACTIONS

- Adult Patients: Common adverse reactions in studies with Noxafil in adults are diarrhea, nausea, fever, vomiting, headache, coughing, and hypokalemia. (6.1)
- Pediatric Patients: Common adverse reactions (incidence >20% receiving 6 mg/kg Noxafil injection and Noxafil PowderMix for delayed-release oral suspension) in a study in pediatric patients are pyrexia, febrile neutropenia, vomiting, mucosal inflammation, pruritus, hypertension, hypokalemia, and stomatitis. (6.1)

To report SUSPECTED ADVERSE REACTIONS, contact Merck Sharp & Dohme LLC at 1-877-888-4231 or FDA at 1-800-FDA-1088 or www.fda.gov/medwatch .

7 DRUG INTERACTIONS

Interaction Drug | Interaction
Rifabutin, phenytoin, efavirenz, cimetidine, esomeprazole [The drug interactions with esomeprazole and metoclopramide do not apply to Noxafil tablets or Noxafil PowderMix (7.3, 12.3).] | Avoid coadministration unless the benefit outweighs the risks (7.1, 7.2)
Other drugs metabolized by CYP3A4 | Consider dosage adjustment and monitor for adverse effects and toxicity (7.2)
Digoxin | Monitor digoxin plasma concentrations (7.2)
Fosamprenavir, metoclopramide | Monitor for breakthrough fungal infections (7.1)

8 USE IN SPECIFIC POPULATIONS

- Pregnancy: Based on animal data, may cause fetal harm. (8.1)
- Pediatrics: Safety and effectiveness in patients younger than 2 years of age have not been established. (8.4)
- Severe Renal Impairment: Monitor closely for breakthrough fungal infections. (8.6)

FULL PRESCRIBING INFORMATION

1 INDICATIONS AND USAGE

1.1 Treatment of Invasive Aspergillosis

Noxafil is indicated for the treatment of invasive aspergillosis as follows:

- Noxafil injection: adults and pediatric patients 2 years of age and older who weigh 10 kg or greater
- Noxafil delayed-release tablets: adults and pediatric patients 2 years of age and older who weigh greater than 40 kg
- Noxafil PowderMix for delayed-release oral suspension: pediatric patients 2 years of age and older who weigh 10 to 40 kg

1.2 Prophylaxis of Invasive Aspergillus and Candida Infections

Noxafil is indicated for the prophylaxis of invasive Aspergillus and Candida infections in patients who are at high risk of developing these infections due to being severely immunocompromised, such as hematopoietic stem cell transplant (HSCT) recipients with graft-versus-host disease (GVHD) or those with hematologic malignancies with prolonged neutropenia from chemotherapy as follows:

- Noxafil injection: adults and pediatric patients 2 years of age and older who weigh 10 kg or greater
- Noxafil delayed-release tablets: adults and pediatric patients 2 years of age and older who weigh greater than 40 kg
- Noxafil oral suspension: adults and pediatric patients 13 years of age and older
- Noxafil PowderMix for delayed-release oral suspension: pediatric patients 2 years of age and older who weigh 10 kg to 40 kg

1.3 Treatment of Oropharyngeal Candidiasis Including Oropharyngeal Candidiasis Refractory to Itraconazole and/or Fluconazole

Noxafil oral suspension is indicated for the treatment of oropharyngeal candidiasis, including oropharyngeal candidiasis refractory to itraconazole and/or fluconazole in adults and pediatric patients 13 years of age and older.

2 DOSAGE AND ADMINISTRATION

2.1 Important Administration Instructions

Noxafil injection, Noxafil delayed-release tablets, Noxafil oral suspension and Noxafil PowderMix for delayed-release oral suspension are supplied in different dose strengths of posaconazole, are approved for different indications, age groups and weights; have different dosages and duration of therapy; and have different preparation and administration instructions.

Therefore, select the recommended dosage form based on the indication, age group, and weight and carefully follow the recommended dosage, preparation and administration instructions described for each product [see Dosage and Administration (2.2 to 2.11)], and the following important administration instructions described below.

Non-substitutable

Noxafil oral suspension is not substitutable with Noxafil delayed-release tablets or Noxafil PowderMix for delayed-release oral suspension due to the differences in the dosing of each formulation. Therefore, follow the specific dosage recommendations for each of the formulations [see Dosage and Administration (2.2, 2.3)].

Noxafil injection

- Administer via a central venous line, including a central venous catheter or peripherally inserted central catheter (PICC), by slow intravenous infusion over approximately 90 minutes [see Dosage and Administration (2.6)].
- Do NOT administer Noxafil injection as an intravenous bolus injection.

Noxafil delayed-release tablets

- Swallow tablets whole. Do not divide, crush, or chew.
- Administer with or without food [see Dosage and Administration (2.7) and Clinical Pharmacology (12.3)].
- For patients who cannot eat a full meal, Noxafil delayed-release tablets should be used instead of Noxafil oral suspension for the prophylaxis indication. Noxafil delayed-release tablets generally provide higher plasma drug exposures than Noxafil oral suspension under both fed and fasted conditions [see Dosage and Administration (2.8)].

Noxafil oral suspension

- Administer with a full meal or with a liquid nutritional supplement or an acidic carbonated beverage (e.g., ginger ale) in patients who cannot eat a full meal [see Dosage and Administration (2.8)].

Noxafil PowderMix for delayed-release oral suspension

- Administer with food [see Clinical Pharmacology (12.3)].
- To ensure delivery of the correct dose, ONLY the provided notched tip syringes must be used for preparation and administration. The design of the notched tip syringe prevents aggregation of the suspension during preparation and administration [see Dosage and Administration (2.10)].

2.2 Recommended Dosage of Noxafil in Adult Patients

The recommended dosage of Noxafil (injection, delayed-release tablets, and oral suspension) in adult patients for the treatment of invasive aspergillosis, prophylaxis of invasive Aspergillus and Candida infections in patients who are at high risk of developing these infections due to being severely immunocompromised, or for the treatment of oropharyngeal candidiasis (OPC) is shown in Table 1 [see Dosage and Administration (2.5, 2.6, 2.7,2.8, 2.9) and Clinical Pharmacology (12.3)].

Noxafil PowderMix for delayed-release oral suspension is not recommended for use in adults [see Indications and Usage (1.1, 1.2)].

Table 1: Recommended Dosage of Noxafil Injection, Noxafil Delayed-Release Tablets, and Noxafil Oral Suspension in Adult Patients
Dosage | Duration of Therapy
Treatment of Invasive Aspergillosis [Switching between the Noxafil injection and delayed-release tablets is acceptable. A loading dose is not required when switching between dosage forms.]
Noxafil Injection:; Loading dose: 300 mg Noxafil injection intravenously twice a day on the first day.; Maintenance dose: 300 mg Noxafil injection intravenously once a day, starting on the second day.; Noxafil Delayed-Release Tablets: Loading dose: 300 mg (three 100 mg delayed-release tablets) twice a day on the first day. Maintenance dose: 300 mg (three 100 mg delayed-release tablets) once a day, starting on the second day. | Loading dose: 1 day; Maintenance dose: Recommended total duration of therapy is 6 to 12 weeks.
Prophylaxis of Invasive Aspergillus and Candida Infections
Noxafil Injection: Loading dose: 300 mg Noxafil injection intravenously twice a day on the first day. Maintenance dose: 300 mg Noxafil injection intravenously once a day thereafter. Noxafil Delayed-Release Tablets: Loading dose: 300 mg (three 100 mg delayed-release tablets) twice a day on the first day. Maintenance dose: 300 mg (three 100 mg delayed-release tablets) once a day, starting on the second day. Noxafil Oral Suspension: 200 mg (5 mL) three times a day. | Loading dose: 1 day Maintenance dose: Duration of therapy is based on recovery from neutropenia or immunosuppression
Oropharyngeal Candidiasis (OPC)
Noxafil Oral Suspension: Loading dose: 100 mg (2.5 mL) twice a day on the first day. Maintenance dose: 100 mg (2.5 mL) once a day thereafter. | Loading dose: 1 day Maintenance dose: 13 days
OPC Refractory (rOPC) to Itraconazole and/or Fluconazole
Noxafil Oral Suspension: 400 mg (10 mL) twice a day. | Duration of therapy is based on the severity of the patient’s underlying disease and clinical response.

2.3 Recommended Dosage of Noxafil for the Treatment of Invasive Aspergillosis and Prophylaxis of Invasive Aspergillus and Candida Infections in Pediatric Patients 2 Years of Age and Older

Noxafil injection and Noxafil delayed-release tablets

The recommended dosage of (1) Noxafil injection in pediatric patients 2 years of age and older who weigh 10 kg or greater, and (2) Noxafil delayed-release tablets in pediatric patients 2 years of age and older who weigh greater than 40 kg for the treatment of invasive aspergillosis and prophylaxis of invasive Aspergillus and Candida infections is shown in Table 2 [see Dosage and Administration (2.5, 2.6, 2.7, 2.9) and Clinical Pharmacology (12.3)].

Noxafil delayed-release tablets are not recommended for use in pediatric patients who weigh 40 kg or less because the recommended dosage cannot be achieved with this dosage form.

Table 2: Recommended Dosage of Noxafil Injection and Noxafil Delayed-Release Tablets for the Treatment of Invasive Aspergillosis [Switching between the intravenous and delayed-release tablets is acceptable. A loading dose is not required when switching between formulations.] and Prophylaxis of Invasive Aspergillus and Candida Infections in Pediatric Patients (2 Years of Age and Older)
Recommended Pediatric Dosage by Formulation | Duration of Therapy
Noxafil Injection (patients weighing 10 kg or greater):; Loading dose: 6 mg/kg up to a maximum of 300 mg twice daily on the first day; Maintenance dose: 6 mg/kg up to a maximum of 300 mg once daily, starting on the second day.; Noxafil Delayed-Release Tablets (patients weighing greater than 40 kg): Loading dose: 300 mg (three 100 mg delayed-release tablets) twice a day on the first day. Maintenance dose: 300 mg (three 100 mg delayed-release tablets) once a day, starting on the second day. | Treatment of invasive aspergillosis: Recommended total duration of therapy is 6 to 12 weeks; Prophylaxis of invasive Aspergillus and Candida infections: Duration of therapy is based on recovery from neutropenia or immunosuppression.

Noxafil Oral Suspension

The recommended dosage of Noxafil oral suspension in pediatric patients 13 years of age and older for the prophylaxis of invasive Aspergillus and Candida Infections is shown in Table 3.

Table 3: Recommended Dosage of Noxafil Oral Suspension for the Prophylaxis of Invasive Aspergillus and Candida Infections in Pediatric Patients (13 Years of Age and Older)
Recommended Pediatric Dosage of Noxafil Oral Suspension | Duration of Therapy
200 mg (5 mL) three times a day | Duration of therapy is based on recovery from neutropenia or immunosuppression.

Noxafil PowderMix

The recommended dosage of Noxafil PowderMix for delayed-release oral suspension in pediatric patients 2 years of age and older who weigh 10 kg to 40 kg, for the treatment of invasive aspergillosis, and the prophylaxis of invasive Aspergillus and Candida infections, is shown in Table 4 and Table 5. The dosing for these indications is the same, except for patients weighing 10 to less than 12 kg [see Dosage and Administration (2.9, 2.10) and Clinical Pharmacology (12.3)].

Noxafil PowderMix for delayed-release oral suspension is not recommended for use in pediatric patients who weigh greater than 40 kg because the recommended dosage cannot be achieved with this dosage form.

Table 4: Recommended Dosage for Noxafil PowderMix for Delayed-Release Oral Suspension for the Treatment of Invasive Aspergillosis in Pediatric Patients (2 Years of Age and Older)
Weight (kg) | Recommended Pediatric Dosage of Noxafil PowderMix for Delayed-Release Oral Suspension | Duration of Therapy
10 to less than 17 | Loading Dose: 120 mg (4 mL) twice daily on the first day Maintenance Dose: 120 mg (4 mL) once daily | Recommended total duration of therapy is 6 to 12 weeks.
17 to less than 21 | Loading Dose: 150 mg (5 mL) twice daily on the first day Maintenance Dose: 150 mg (5 mL) once daily | Recommended total duration of therapy is 6 to 12 weeks.
21 to less than 26 | Loading Dose: 180 mg (6 mL) twice daily on the first day Maintenance Dose: 180 mg (6 mL) once daily | Recommended total duration of therapy is 6 to 12 weeks.
26 to less than 36 | Loading Dose: 210 mg (7 mL) twice daily on the first day Maintenance Dose: 210 mg (7 mL) once daily | Recommended total duration of therapy is 6 to 12 weeks.
36 to 40 | Loading Dose: 240 mg (8 mL) twice daily on the first day Maintenance Dose: 240 mg (8 mL) once daily | Recommended total duration of therapy is 6 to 12 weeks.

Table 5: Recommended Dosage for Noxafil PowderMix for Delayed-Release Oral Suspension for the Prophylaxis of Invasive Aspergillus and Candida infections in Pediatric Patients (2 Years of Age and Older)
Weight (kg) | Recommended Pediatric Dosage of Noxafil PowderMix for Delayed-Release Oral Suspension | Duration of Therapy
10 to less than 12 | Loading Dose: 90 mg (3 mL) twice daily on the first day Maintenance Dose: 90 mg (3 mL) once daily | Duration of therapy is based on recovery from neutropenia or immunosuppression.
12 to less than 17 | Loading Dose: 120 mg (4 mL) twice daily on the first day Maintenance Dose: 120 mg (4 mL) once daily | Duration of therapy is based on recovery from neutropenia or immunosuppression.
17 to less than 21 | Loading Dose: 150 mg (5 mL) twice daily on the first day Maintenance Dose: 150 mg (5 mL) once daily | Duration of therapy is based on recovery from neutropenia or immunosuppression.
21 to less than 26 | Loading Dose: 180 mg (6 mL) twice daily on the first day Maintenance Dose: 180 mg (6 mL) once daily | Duration of therapy is based on recovery from neutropenia or immunosuppression.
26 to less than 36 | Loading Dose: 210 mg (7 mL) twice daily on the first day Maintenance Dose: 210 mg (7 mL) once daily | Duration of therapy is based on recovery from neutropenia or immunosuppression.
36 to 40 | Loading Dose: 240 mg (8 mL) twice daily on the first day Maintenance Dose: 240 mg (8 mL) once daily | Duration of therapy is based on recovery from neutropenia or immunosuppression.

2.4 Recommended Dosage of Noxafil Oral Suspension for the Treatment of Oropharyngeal Candidiasis in Pediatric Patients 13 Years of Age and Older

The recommended dosage of Noxafil oral suspension for the treatment of oropharyngeal candidiasis (OPC) and OPC refractory (rOPC) to itraconazole and/or fluconazole in pediatric patients 13 years of age and older is shown in Table 6.

The Noxafil injection, Noxafil delayed-release tablets, and Noxafil PowderMix for delayed-release oral suspension products are not approved for the treatment of oropharyngeal candidiasis in pediatric patients.

Table 6: Recommended Dosage of Noxafil Oral Suspension for the Treatment of OPC and rOPC in Pediatric Patients (13 Years of Age and Older)
Recommended Pediatric Dosage of Noxafil Oral Suspension | Duration of Therapy
Oropharyngeal Candidiasis (OPC)
Loading Dose: 100 mg (2.5 mL) twice daily on the first day; Maintenance Dose: 100 mg (2.5 mL) once daily | Loading dose: 1 day; Maintenance dose: 13 days
OPC Refractory (rOPC) to Itraconazole and/or Fluconazole
400 mg (10 mL) twice daily | Duration of therapy is based on the severity of the patient’s underlying disease and clinical response.

2.5 Preparation of Noxafil Injection

Preparation of Noxafil Injection:

- Remove the vial of Noxafil injection from the refrigerator and allow to equilibrate to room temperature prior to use.
- To prepare the required dose, aseptically transfer one vial of Noxafil injection (containing 300 mg of posaconazole in 16.7 mL of solution) to an intravenous bag or bottle of one of the following compatible diluents to achieve a final posaconazole concentration between 1 mg/mL and 2 mg/mL:
  - 0.45% Sodium Chloride Injection
  - 0.9% Sodium Chloride Injection
  - 5% Dextrose Injection
  - 5% Dextrose and 0.45% Sodium Chloride Injection
  - 5% Dextrose and 0.9% Sodium Chloride Injection
  - 5% Dextrose and 20 mEq Potassium Chloride Injection

Use of other diluents is not recommended because they may result in particulate formation.

- Discard any unused Noxafil injection from the vial.
- Parenteral drug products should be inspected visually for particulate matter prior to administration, whenever solution and container permit. Once admixed, the diluted Noxafil infusion solution ranges from colorless to yellow (variations of color within this range do not affect the quality of the product).
- Immediately use the diluted Noxafil infusion solution, once admixed. If not used immediately, refrigerate (2 to 8°C (36 to 46°F)) the diluted Noxafil infusion solution up to 24 hours. Discard any unused portion.

Incompatible Diluents

Co-administration of drug products besides the infusion solutions or products stated above are not recommended because this may result in particulate formation. The following diluents were determined to be incompatible with Noxafil injection; thus, do not dilute Noxafil injection with them:

- Lactated Ringer’s Injection
- Lactated Ringer's and 5% Dextrose Injection
- 4.2% Sodium Bicarbonate Injection

2.6 Administration of Diluted Noxafil Infusion Solution

See Dosage and Administration (2.5) for the preparation instructions for the diluted Noxafil Solution.

Important Administration Instructions for the Diluted Noxafil Infusion Solution

- Must administer diluted Noxafil Infusion Solution through a 0.22-micron polyethersulfone (PES) or polyvinylidene difluoride (PVDF) filter.
- Administer diluted Noxafil infusion solution via a central venous line, including a central venous catheter (CVC) or peripherally inserted central catheter (PICC), by slow intravenous infusion over approximately 90 minutes [see Adverse Reactions (6.1)]
- If a CVC or PICC are not available, may administer diluted Noxafil solution once through a peripheral venous catheter by intravenous infusion over approximately 30 minutes to bridge the period during which a CVC or PICC are replaced, inserted, or unavailable for use (e.g., the CVC is being used for intravenous treatment with another product). However, do not administer diluted Noxafil infusion solution more than once via peripheral venous catheter because in clinical trials, multiple peripheral infusions given through the same vein resulted in infusion site reactions [see Adverse Reactions (6.1)].
- When multiple dosing is required, the infusion should be done via a central venous line.

Additional Administration Instructions for the Diluted Noxafil Infusion Solution

- Administer diluted Noxafil infusion solution intravenously through the same intravenous line (or cannula) with the following compatible infusion solutions:
  - 0.45% Sodium Chloride Injection
  - 0.9% Sodium Chloride Injection
  - 5% Dextrose Injection
  - 5% Dextrose and 0.45% Sodium Chloride Injection
  - 5% Dextrose and 0.9% Sodium Chloride Injection
  - 5% Dextrose and 20 mEq potassium chloride Injection
- Administer diluted Noxafil infusion solution intravenously at the same time through the same intravenous line (or cannula) with the following intravenous drug products prepared in 5% Dextrose Injection or 0.9% Sodium Chloride Injection:
  - Amikacin Sulfate Injection
  - Caspofungin Acetate for Injection
  - Ciprofloxacin Injection
  - Daptomycin for Injection
  - Dobutamine Injection
  - Famotidine Injection
  - Filgrastim Injection
  - Gentamicin Injection
  - Hydromorphone Hydrochloride Injection
  - Levofloxacin Injection
  - Lorazepam Injection
  - Meropenem for Injection
  - Micafungin for Injection
  - Morphine Sulfate Injection
  - Norepinephrine Bitartrate Injection
  - Potassium Chloride Injection
  - Vancomycin Hydrochloride for Injection

2.7 Administration Instructions for Noxafil Delayed-Release Tablets

- Swallow the Noxafil delayed-release tablets whole. Do not divide, crush, or chew.
- Administer Noxafil delayed-release tablets orally with or without food [see Clinical Pharmacology (12.3)].

2.8 Administration Instructions for Noxafil Oral Suspension

Administer Noxafil oral suspension with a full meal or with a liquid nutritional supplement or an acidic carbonated beverage (e.g., ginger ale) in patients who cannot eat a full meal.

For patients who cannot eat a full meal, use Noxafil delayed-release tablets instead of the Noxafil oral suspension for the prophylaxis of invasive Aspergillus and Candida infections in those who are at high risk of developing these infections due to being severely immunocompromised. This is because Noxafil delayed-release tablets provide higher plasma drug exposures than Noxafil oral suspension under fasted condition [see Dosage and Administration (2.1)].

For those patients using the Noxafil oral suspension:

- Shake Noxafil oral suspension well before use.
- Administer with measured dosing spoon provided in the package (see Figure 1).

Figure 1: Measured dosing spoon provided in the package marked for doses of 2.5 mL and 5 mL.

- Administer each dose of Noxafil oral suspension during or immediately (i.e., within 20 minutes) following a full meal [see Clinical Pharmacology (12.3)].
- In patients who cannot eat a full meal and for whom Noxafil delayed-release tablets or Noxafil injection are not options, administer each dose of Noxafil oral suspension with a liquid nutritional supplement or an acidic carbonated beverage (e.g., ginger ale). If these patients cannot tolerate an oral nutritional supplement or an acidic carbonated beverage either use:
  - An alternative antifungal therapy, or
  - Noxafil oral suspension and closely monitor patients for breakthrough fungal infections.
- Rinse the spoon with water after each administration and before storage.

2.9 Non-substitutability between Noxafil Oral Suspension and Other Formulations

Noxafil oral suspension is not substitutable with Noxafil delayed-release tablets or Noxafil PowderMix for delayed-release oral suspension due to the differences in the dosing of each formulation. Therefore, follow the specific dosage recommendations for each of the formulations [see Dosage and Administration (2.2, 2.3)].

2.10 Preparation and Administration Instructions for Noxafil PowderMix for Delayed-Release Oral Suspension

For details on preparation and administration of Noxafil PowderMix for delayed-release oral suspension, see Instructions for Use.

Preparation Instructions for Noxafil PowderMix for Delayed-Release Oral Suspension

- Do not open the Noxafil PowderMix packet until ready to prepare the drug.
- Remove cap from the mixing liquid and push the bottle adapter into the neck of the bottle. Once in place, the bottle adapter stays in the bottle.
- Remove 9 mL of mixing liquid using the provided blue syringe. Put the cap back on the bottle.Only use the mixing liquid in the kit to prepare Noxafil PowderMix.
- Using the provided mixing cup, combine 9 mL of mixing liquid and the entire contents of one packet in the Noxafil PowderMix kit and mix (containing 300 mg of posaconazole).
- Shake the mixing cup vigorously for 45 seconds to mix the powder and mixing liquid from the Noxafil PowderMix kit. The final concentration of the reconstituted Noxafil PowderMix delayed-release suspension is approximately 30 mg/mL of posaconazole. Check to make sure the powder is mixed (the mixture should look cloudy and free of clumps).
- Must use the reconstituted Noxafil PowderMix delayed-release suspension within 1 hour of reconstitution. Discard unused portion of the reconstituted Noxafil PowderMix delayed-release suspension.

Administration Instructions for Noxafil PowderMix Delayed-Release Reconstituted Suspension

- To ensure delivery of the correct reconstituted Noxafil PowderMix Delayed-release dose, only use the provided notched tip syringes for preparation and administration because its design reduces the risk of aggregation of the product during preparation and administration.
- Choose the correct syringe based on the prescribed Noxafil PowderMix dose:
  - Use 3 mL (green) notched tip syringe (provided with the kit) if dose is 3 mL or less.
  - Use 10 mL (blue) notched tip syringe (provided with the kit) if dose is more than 3 mL.
- Administer reconstituted Noxafil PowderMix suspension orally with food within 1 hour of reconstitution [see Clinical Pharmacology (12.3)].
- The maximum dose that can be accurately withdrawn from the mixing cup after reconstitution is 240 mg (8 mL).

Discarding Unused Reconstituted Noxafil PowderMix Suspension and Reuse of Syringes

- Not all the reconstituted Noxafil PowderMix suspension in the mixing cup will be used; there will be some left over in the mixing cup.
- Discard any remaining reconstituted Noxafil PowderMix suspension.
- The mixing cup may be hand washed and reused. Alternatively, the mixing cup may be discarded, and a similar mixing cup with a lid may be used for subsequent doses.
- The notched tip syringes may be hand washed and reused.

2.11 Dosage Modifications in Patients with Renal Impairment

The recommended dosage of Noxafil oral suspension, Noxafil delayed-release tablets, and Noxafil PowderMix for delayed-release oral suspension is the same in patients with renal impairment compared to those with normal renal function.

Avoid the use of Noxafil injection in patients with eGFR less than 50 mL/minute/1.73 m^2, unless an assessment of the benefit/risk to the patient justifies its use. If the decision is made to use Noxafil injection in patients with eGFR less than 50 mL/minute/1.73 m^2, closely monitor serum creatinine levels, and, if increases occur, consider changing to oral Noxafil therapy. The recommended dosage of Noxafil injection in patients with eGFR 50 to 90 mL/minute/1.73 m^2 is the same as those with normal renal function.

3 DOSAGE FORMS AND STRENGTHS

Noxafil injection

300 mg/16.7 mL (18 mg/mL) of posaconazole: Clear, colorless to yellow sterile liquid in a single-dose vial.

Noxafil Delayed-Release Tablets

100 mg of posaconazole: Yellow, coated, oblong tablets, debossed with "100" on one side.

Noxafil Oral Suspension

4,200 mg/105 mL (40 mg/mL) of posaconazole: White, cherry-flavored suspension in amber glass bottles with child-resistant closures.

Noxafil PowderMix for Delayed-Release Oral Suspension

300 mg: Off-white to yellowish powder for delayed-release oral suspension and a mixing liquid in a kit. The kit contains (1) Package A that contains single-use packets of Noxafil PowderMix, green notched tip syringes, blue notched tip syringes, mixing cups, mixing liquid bottle, and one bottle adapter for the mixing liquid bottle; and (2) Package B that contains green and blue notched tip syringes for additional supply [see How Supplied/Storage and Handling (16.1)].

4 CONTRAINDICATIONS

4.1 Hypersensitivity

Noxafil is contraindicated in persons with known hypersensitivity to posaconazole or other azole antifungal agents.

4.2 Use with Sirolimus

Noxafil is contraindicated with sirolimus. Concomitant administration of Noxafil with sirolimus increases the sirolimus blood concentrations by approximately 9-fold and can result in sirolimus toxicity [see Drug Interactions (7.2) and Clinical Pharmacology (12.3)].

4.3 QT Prolongation with Concomitant Use with CYP3A4 Substrates

Noxafil is contraindicated with CYP3A4 substrates that prolong the QT interval. Concomitant administration of Noxafil with the CYP3A4 substrates, pimozide and quinidine may result in increased plasma concentrations of these drugs, leading to QTc prolongation and cases of torsades de pointes [see Warnings and Precautions (5.2) and Drug Interactions (7.2)].

4.4 HMG-CoA Reductase Inhibitors Primarily Metabolized Through CYP3A4

Coadministration with the HMG-CoA reductase inhibitors that are primarily metabolized through CYP3A4 (e.g., atorvastatin, lovastatin, and simvastatin) is contraindicated since increased plasma concentration of these drugs can lead to rhabdomyolysis [see Drug Interactions (7.2) and Clinical Pharmacology (12.3)].

4.5 Use with Ergot Alkaloids

Noxafil may increase the plasma concentrations of ergot alkaloids (ergotamine and dihydroergotamine) which may lead to ergotism [see Drug Interactions (7.2)].

4.6 Use with Venetoclax

Coadministration of Noxafil with venetoclax at initiation and during the ramp-up phase is contraindicated in patients with chronic lymphocytic leukemia (CLL) or small lymphocytic lymphoma (SLL) due to the potential for increased risk of tumor lysis syndrome [see Warnings and Precautions (5.11) and Drug Interactions (7.2)].

4.7 Use of Noxafil PowderMix for Delayed-Release Oral Suspension in Patients with Hereditary Fructose Intolerance

Noxafil PowderMix for delayed-release oral suspension is contraindicated in patients with known or suspected hereditary fructose intolerance (HFI) [see Warnings and Precautions (5.9) and Use in Specific Populations (8.4)].

5 WARNINGS AND PRECAUTIONS

5.1 Calcineurin-Inhibitor Toxicity

Concomitant administration of Noxafil with cyclosporine or tacrolimus increases the whole blood trough concentrations of these calcineurin-inhibitors [see Drug Interactions (7.2) and Clinical Pharmacology (12.3)]. Nephrotoxicity and leukoencephalopathy (including deaths) have been reported in clinical efficacy studies in patients with elevated cyclosporine or tacrolimus concentrations. Frequent monitoring of tacrolimus or cyclosporine whole blood trough concentrations should be performed during and at discontinuation of Noxafil treatment and the tacrolimus or cyclosporine dose adjusted accordingly.

5.2 Arrhythmias and QT Prolongation

Some azoles, including Noxafil, have been associated with prolongation of the QT interval on the electrocardiogram. In addition, cases of torsades de pointes have been reported in patients taking Noxafil.

Results from a multiple time-matched ECG analysis in healthy volunteers did not show any increase in the mean of the QTc interval. Multiple, time-matched ECGs collected over a 12-hour period were recorded at baseline and steady-state from 173 healthy male and female volunteers (18-85 years of age) administered Noxafil oral suspension 400 mg twice daily with a high-fat meal. In this pooled analysis, the mean QTc (Fridericia) interval change from baseline was –5 msec following administration of the recommended clinical dose. A decrease in the QTc(F) interval (–3 msec) was also observed in a small number of subjects (n=16) administered placebo. The placebo-adjusted mean maximum QTc(F) interval change from baseline was <0 msec (–8 msec). No healthy subject administered Noxafil had a QTc(F) interval ≥500 msec or an increase ≥60 msec in their QTc(F) interval from baseline.

Noxafil should be administered with caution to patients with potentially proarrhythmic conditions. Do not administer with drugs that are known to prolong the QTc interval and are metabolized through CYP3A4 [see Contraindications (4.3) and Drug Interactions (7.2)].

5.3 Electrolyte Disturbances

Electrolyte disturbances, especially those involving potassium, magnesium or calcium levels, should be monitored and corrected as necessary before and during Noxafil therapy.

5.4 Pseudoaldosteronism

Pseudoaldosteronism, manifested by the onset of hypertension or worsening of hypertension, and abnormal laboratory findings (hypokalemia, low serum renin and aldosterone, and elevated 11-deoxycortisol), has been reported with posaconazole use in the postmarket setting. Monitor blood pressure and potassium levels and manage as necessary. Management of pseudoaldosteronism may include discontinuation of Noxafil, substitution with an appropriate antifungal drug that is not associated with pseudoaldosteronism, or use of aldosterone receptor antagonists.

5.5 Hepatic Toxicity

Hepatic reactions (e.g., mild to moderate elevations in alanine aminotransferase (ALT), aspartate aminotransferase (AST), alkaline phosphatase, total bilirubin, and/or clinical hepatitis) have been reported in clinical trials. The elevations in liver tests were generally reversible on discontinuation of therapy, and in some instances these tests normalized without drug interruption. Cases of more severe hepatic reactions including cholestasis or hepatic failure including deaths have been reported in patients with serious underlying medical conditions (e.g., hematologic malignancy) during treatment with Noxafil. These severe hepatic reactions were seen primarily in subjects receiving the Noxafil oral suspension 800 mg daily (400 mg twice daily or 200 mg four times a day) in clinical trials.

Liver tests should be evaluated at the start of and during the course of Noxafil therapy. Patients who develop abnormal liver tests during Noxafil therapy should be monitored for the development of more severe hepatic injury. Patient management should include laboratory evaluation of hepatic function (particularly liver tests and bilirubin). Discontinuation of Noxafil must be considered if clinical signs and symptoms consistent with liver disease develop that may be attributable to Noxafil.

5.6 Renal Impairment

Due to the variability in exposure with Noxafil delayed-release tablets, Noxafil oral suspension, and Noxafil PowderMix for delayed-release oral suspension, patients with severe renal impairment should be monitored closely for breakthrough fungal infections [see Dosage and Administration (2.11) and Use in Specific Populations (8.6)].

Noxafil injection should be avoided in patients with moderate or severe renal impairment (eGFR <50 mL/min/1.73 m^2), unless an assessment of the benefit/risk to the patient justifies the use of Noxafil injection. In patients with moderate or severe renal impairment (eGFR <50 mL/min/1.73 m^2), receiving the Noxafil injection, accumulation of the intravenous vehicle, SBECD, is expected to occur. Serum creatinine levels should be closely monitored in these patients, and, if increases occur, consideration should be given to changing to oral Noxafil therapy [see Dosage and Administration (2.11) and Use in Specific Populations (8.6)].

5.7 Midazolam Toxicity

Concomitant administration of Noxafil with midazolam increases the midazolam plasma concentrations by approximately 5-fold. Increased plasma midazolam concentrations could potentiate and prolong hypnotic and sedative effects. Patients must be monitored closely for adverse effects associated with high plasma concentrations of midazolam and benzodiazepine receptor antagonists must be available to reverse these effects [see Drug Interactions (7.2) and Clinical Pharmacology (12.3)].

5.8 Vincristine Toxicity

Concomitant administration of azole antifungals, including Noxafil, with vincristine has been associated with neurotoxicity and other serious adverse reactions, including seizures, peripheral neuropathy, syndrome of inappropriate antidiuretic hormone secretion, and paralytic ileus. Reserve azole antifungals, including Noxafil, for patients receiving a vinca alkaloid, including vincristine, who have no alternative antifungal treatment options [see Drug Interactions (7.2)].

5.9 Risk in Patients with Hereditary Fructose Intolerance (HFI)

Noxafil PowderMix for delayed-release oral suspension contains sorbitol, an inactive ingredient, and may precipitate a metabolic crisis that may include, but is not limited to life-threatening hypoglycemia, hypophosphatemia, lactic acidosis, and hepatic failure in patients with HFI. Obtain careful history of HFI symptoms (nausea, vomiting, abdominal pain) with sorbitol/fructose/sucrose exposure prior to Noxafil PowderMix for delayed-release oral suspension administration because a diagnosis of HFI may not yet be established in pediatric patients [see Contraindications (4) and Use in Specific Populations (8.4)].

5.10 Breakthrough Fungal Infections

Patients who have severe diarrhea or vomiting should be monitored closely for breakthrough fungal infections when receiving Noxafil delayed-release tablets, Noxafil oral suspension, or Noxafil PowderMix for delayed-release oral suspension.

5.11 Venetoclax Toxicity

Concomitant administration of Noxafil, a strong CYP3A4 inhibitor, with venetoclax may increase venetoclax toxicities, including the risk of tumor lysis syndrome (TLS), neutropenia, and serious infections. In patients with CLL/SLL, administration of Noxafil during initiation and the ramp-up phase of venetoclax is contraindicated [see Contraindications (4.6)]. Refer to the venetoclax labeling for safety monitoring and dose reduction in the steady daily dosing phase in CLL/SLL patients.

For patients with acute myeloid leukemia (AML), dose reduction and safety monitoring are recommended across all dosing phases when coadministering Noxafil with venetoclax [see Drug Interactions (7.2)]. Refer to the venetoclax prescribing information for dosing instructions.

6 ADVERSE REACTIONS

The following serious and otherwise important adverse reactions are discussed in detail in another section of the labeling:

- Arrhythmias and QT Prolongation [see Warnings and Precautions (5.2)]
- Electrolyte Disturbances [see Warnings and Precautions (5.3)]
- Pseudoaldosteronism [see Warnings and Precautions (5.4)]
- Hepatic Toxicity [see Warnings and Precautions (5.5)]

6.1 Clinical Trials Experience

Because clinical trials are conducted under widely varying conditions, adverse reaction rates observed in clinical trials of Noxafil cannot be directly compared to rates in the clinical trials of another drug and may not reflect the rates observed in practice.

Treatment of Invasive Aspergillosis in Adults and Adolescents (Noxafil injection and Noxafil Delayed-Release Tablets)

The safety of Noxafil injection and Noxafil delayed-release tablets was assessed in a randomized, double-blind, active-controlled clinical study of Noxafil injection and Noxafil delayed-release tablets versus voriconazole for treatment of invasive aspergillosis (Aspergillosis Treatment Study). A total of 575 adult and pediatric patients 14 years of age and older (288 in the Noxafil group, 287 in voriconazole group (voriconazole for injection or voriconazole tablets)) with proven, probable or possible invasive aspergillosis were included. The median duration of treatment was 67 days for Noxafil injection or Noxafil delayed-release tablets and 64 days for voriconazole. In this study, 55% to 60% of patients started intravenous treatment with Noxafil (Noxafil injection) or voriconazole (voriconazole for injection). The median duration of the first instance of intravenous treatment (before switching to oral treatment or discontinuing or completing study treatment) was 9 days for both groups. Table 7 presents adverse reactions reported at an incidence of ≥10% in either one of the treatment groups in the Aspergillosis Treatment Study.

Adverse reactions leading to treatment discontinuation were reported for 34% of patients. The most commonly reported adverse reactions (>2% of patients) leading to treatment discontinuation were septic shock, respiratory failure, and bronchopulmonary aspergillosis in the Noxafil group, and septic shock and acute myeloid leukemia in the voriconazole group. The most frequently reported adverse reactions in the Noxafil-treated group were pyrexia (28%), hypokalemia (28%), and nausea (23%).

Table 7: Adverse Reactions in at least 10% of Adults and Adolescents Receiving Noxafil Injection or Noxafil Delayed-Release Tablets for the Treatment of Invasive Aspergillosis
Adverse Reactions | Noxafil injection or Noxafil delayed-release tablets n=288 (%) | Voriconazole for injection or Voriconazole tablets n=287 (%)
Percentage of Patients Reporting any Adverse Reaction | 97.6 | 97.6
Hypokalemia | 28.5 | 17.1
Pyrexia | 28.1 | 25.1
Nausea | 22.6 | 17.8
Diarrhea | 18.1 | 18.1
Vomiting | 18.1 | 13.6
Alanine aminotransferase increased | 14.6 | 12.9
Febrile neutropenia | 14.6 | 13.2
Aspartate aminotransferase increased | 13.2 | 12.5
Pneumonia | 12.5 | 9.1
Headache | 12.2 | 8.7
Constipation | 11.1 | 8.0
Edema peripheral | 11.1 | 8.4
Epistaxis | 11.1 | 5.9
Cough | 10.4 | 8.4
Abdominal pain | 10.1 | 8.4
Hypomagnesemia | 10.1 | 6.3

Clinical Trial Experience with Noxafil Injection for Prophylaxis of Invasive Aspergillus and Candida Infections

Administration of multiple doses of Noxafil injection via a peripheral venous catheter were associated with thrombophlebitis (60% incidence). Therefore, in subsequent studies, Noxafil injection was administered via central venous catheter [see Dosage and Administration (2.6)].

The safety of Noxafil injection has been assessed in 268 patients in a clinical trial. Patients were enrolled in a non-comparative pharmacokinetic and safety trial of Noxafil injection when given as antifungal prophylaxis (Noxafil Injection Study). Patients were immunocompromised with underlying conditions including hematological malignancy, neutropenia post-chemotherapy, GVHD, and post HSCT. This patient population was 55% male, had a mean age of 51 years (range: 18-82 years, 19% of patients were ≥65 years of age), and were 95% White and 8% Hispanic. In this study, 10 patients received a single dose of 200 mg Noxafil injection, 21 patients received 200 mg daily dosage for a median of 14 days, and 237 patients received 300 mg daily dosage for a median of 9 days (the 200 mg dosage is not a recommended dosage for prophylaxis of invasive Aspergillus and Candida infections in adults [see Dosage and Administration (2.2)]. In the 300 mg daily dosage group each patient received a loading intravenous dose of Noxafil injection 300 mg twice on Day 1, then intravenous Noxafil injection therapy, and finally Noxafil oral suspension to complete 28 days of total Noxafil therapy.

Table 8 presents adverse reactions observed in patients treated with the Noxafil injection 300 mg daily dosage group in the Noxafil Injection Study.

The most frequently reported adverse reactions with an onset during the intravenous Noxafil injection phase of dosing with 300 mg once daily were diarrhea (32%), hypokalemia (22%), pyrexia (21%), and nausea (19%). These adverse reactions were consistent with those seen in studies with Noxafil oral suspension.

Table 8: Adverse Reactions in at least 10% of Adults Receiving Noxafil Injection for the Prophylaxis of Invasive Aspergillus and Candida infections
Adverse Reactions | Noxafil Injection Treatment Phase n=237 [Adverse reactions reported in patients with an onset during the Noxafil intravenous dosing phase of the study.] (%) | Noxafil Injection Treatment Phase or Subsequent Noxafil Oral Suspension Treatment Phase n=237 [Adverse reactions reported with an onset at any time during the study in patients who were treated for up to 28 days of Noxafil therapy.] (%)
Percentage of Patients Reporting any Adverse Reaction | 93 | 99
Diarrhea | 32 | 39
Hypokalemia | 22 | 28
Pyrexia | 21 | 31
Nausea | 19 | 30
Rash | 15 | 24
Headache | 14 | 21
Epistaxis | 14 | 17
Abdominal Pain | 13 | 17
Chills | 12 | 16
Edema Peripheral | 12 | 15
Vomiting | 12 | 19
Hypomagnesemia | 11 | 13
Decreased appetite | 10 | 12
Cough | 9 | 13
Constipation | 8 | 13
Fatigue | 8 | 10
Hypertension | 8 | 11
Petechiae | 8 | 10
Anemia | 7 | 10
Dyspnea | 7 | 10
Thrombocytopenia | 7 | 11
Abdominal Pain Upper | 6 | 11

Clinical Trial Experience with Noxafil Delayed-Release Tablets for Prophylaxis of Invasive Aspergillus and Candida Infections

The safety of Noxafil delayed-release tablets has been assessed in 230 patients in clinical trials. Patients were enrolled in a non-comparative pharmacokinetic and safety trial of Noxafil delayed-release tablets when given as antifungal prophylaxis (Noxafil Delayed-Release Tablet Study). Patients were immunocompromised with underlying conditions including hematological malignancy, neutropenia post-chemotherapy, GVHD, and post HSCT. This patient population was 62% male, had a mean age of 51 years (range: 19-78 years, 17% of patients were ≥65 years of age), and were 93% White and 16% Hispanic. Noxafil delayed-release tablets were given for a median duration of 28 days. In this study, 20 adult patients received 200 mg daily dosage (this is not a recommended dosage [see Dosage and Administration (2.2)]) and 210 adult patients received 300 mg daily dosage (following twice daily dosing on Day 1 in each cohort). Table 9 presents adverse reactions (incidence of ≥ 10%) observed in patients treated with the Noxafil delayed-release tablets 300 mg daily dosage in the Noxafil Delayed-Release Tablet Study.

The most frequently reported adverse reactions (>25%) in patients treated with Noxafil delayed-release tablets 300 mg once daily were diarrhea, pyrexia, and nausea. The most common adverse reaction leading to discontinuation of Noxafil delayed-release tablets 300 mg once daily was nausea (2%).

Table 9: Adverse Reactions in at least 10% of Adults Receiving Noxafil Delayed-Release Tablets (300 mg Daily Dosage) for the Prophylaxis of Invasive Aspergillus and Candida infections
Adverse Reactions | Noxafil delayed-release tablet (300 mg) n=210 (%)
Percentage of Patients Reporting any Adverse Reaction | 99
Diarrhea | 29
Pyrexia | 28
Nausea | 27
Hypokalemia | 22
Cough | 17
Edema Peripheral | 16
Rash | 16
Epistaxis | 14
Headache | 14
Mucosal Inflammation | 14
Thrombocytopenia | 14
Vomiting | 13
Abdominal Pain | 11
Hypertension | 11
Anemia | 10
Asthenia | 10
Chills | 10
Constipation | 10
Hypomagnesemia | 10

Clinical Trials Safety Experience with Noxafil Oral Suspension

The safety of Noxafil oral suspension has been assessed in 1,844 patients, including:

- 605 patients in the active-controlled studies for the prophylaxis of invasive Aspergillus and Candida infections
- 557 patients in the active-controlled OPC studies (not refractory to itraconazole or fluconazole)
- 239 patients in refractory OPC studies (refractory to itraconazole or fluconazole) (rOPC), and
- 443 patients in other patient populations

These studies included immunocompromised patients (e.g., patients with hematological malignancy, neutropenia post-chemotherapy, GVHD post HSCT, and HIV infection), as well as non-neutropenic patients. This patient population was 71% male, had a mean age of 42 years (range: 8-84 years, 6% of patients were ≥65 years of age and 1% was <18 years of age), and were 64% White, 14% Black, 16% Hispanic. Noxafil oral suspension therapy was given to 171 patients for ≥6 months, including 58 patients who received Noxafil oral suspension therapy for ≥12 months. Table 10 presents adverse reactions observed at an incidence of >10% in the studies for prophylaxis of invasive Aspergillus and Candida infections. Table 11 presents adverse reactions observed at an incidence of at least 10% in the OPC/rOPC studies.

Prophylaxis of Invasive Aspergillus and Candida Infections (Noxafil oral suspension)

In the two randomized, comparative studies for prophylaxis of invasive Aspergillus and Candida infections in those at high risk of developing these infections due to being severely immunocompromised (Noxafil Oral Suspension Study 1 and 2), the safety of Noxafil oral suspension 200 mg three times a day was compared to fluconazole 400 mg once daily or itraconazole 200 mg twice a day in severely immunocompromised patients. The most frequently reported adverse reactions (>30%) in these trials were fever, diarrhea, and nausea. The most common adverse reactions leading to discontinuation of Noxafil oral suspension were GI adverse reactions, specifically, nausea (2%), vomiting (2%), and increased hepatic enzymes (2%).

Table 10: Adverse Reactions in at least 10% of Patients Receiving Noxafil Oral Suspension for the Prophylaxis of Invasive Aspergillus and Candida Infections
Adverse Reactions | Noxafil Oral Suspension n=605 (%) | Fluconazole n=539 (%) | Itraconazole n=58 (%)
Percentage of Patients Reporting any Adverse Reaction | 98 | 99 | 100
Fever | 45 | 47 | 55
Diarrhea | 42 | 39 | 60
Nausea | 38 | 37 | 52
Hypokalemia | 30 | 26 | 52
Thrombocytopenia | 29 | 27 | 34
Vomiting | 29 | 32 | 41
Headache | 28 | 26 | 40
Abdominal Pain | 27 | 27 | 36
Anemia | 25 | 23 | 28
Coughing | 24 | 24 | 24
Neutropenia | 23 | 23 | 40
Constipation | 21 | 17 | 17
Dyspnea | 20 | 22 | 26
Rigors | 20 | 16 | 29
Rash | 19 | 18 | 43
Hypertension | 18 | 16 | 5
Hypomagnesemia | 18 | 16 | 19
Fatigue | 17 | 18 | 9
Insomnia | 17 | 17 | 19
Musculoskeletal Pain | 16 | 15 | 16
Anorexia | 15 | 17 | 28
Edema Legs | 15 | 12 | 19
Epistaxis | 14 | 14 | 21
Hypotension | 14 | 15 | 17
Pharyngitis | 12 | 11 | 21
Tachycardia | 12 | 14 | 5
Arthralgia | 11 | 12 | 9
Dizziness | 11 | 10 | 9
Hyperglycemia | 11 | 14 | 3
Petechiae | 11 | 10 | 16
Pruritus | 11 | 12 | 19
Back Pain | 10 | 12 | 7
Bilirubinemia | 10 | 9 | 19
Dyspepsia | 10 | 9 | 10
Vaginal Hemorrhage [Percentages of sex-specific adverse reactions are based on the number of males/females.] | 10 | 9 | 12

Treatment of Nonrefractory OPC and Refractory OPC (Noxafil oral suspension)

In two randomized comparative studies for the treatment of nonrefractory OPC, the safety of Noxafil oral suspension (less than or equal to 400 mg once daily) in 557 HIV-infected patients was compared to the safety of fluconazole (100 mg once daily) in 262 HIV-infected patients.

An additional 239 HIV-infected patients with refractory OPC (rOPC) received Noxafil oral suspension in two non-comparative trials for rOPC. Of these patients, 149 received the 800 mg/day dosage and the remainder received the less than or equal to 400 mg once daily dosage.

In the nonrefractory OPC and rOPC studies, the most common adverse reactions in patients treated with Noxafil oral suspension were fever, diarrhea, nausea, headache, vomiting, and coughing.

Adverse reactions were reported more frequently in the studies of patients with refractory OPC. Among these highly immunocompromised patients with advanced HIV disease, serious adverse reactions were reported in 55% (132/239) of Noxafil oral suspension-treated patients. The most commonly reported serious adverse reactions were fever (13%) and neutropenia (10%).

Table 11: Adverse Reactions in at least 10% of Patients Receiving Noxafil Oral Suspension for the Treatment of Nonrefractory and Refractory OPC
Adverse Reactions
Adverse Reactions | Controlled OPC Pool |  | Refractory OPC Pool
Adverse Reactions | Noxafil Oral Suspension | Fluconazole | Noxafil Oral Suspension
Adverse Reactions | n=557 (%) | n=262 (%) | n=239 (%)
Percentage of Patients that Reported any Adverse Reaction [Based on patients reporting adverse reactions at least once during the study, without regard to relationship to treatment. Patients may have reported more than 1 adverse reaction.] | 64 | 67 | 92
Diarrhea | 10 | 13 | 29
Nausea | 9 | 11 | 29
Headache | 8 | 9 | 20
Vomiting | 7 | 7 | 28
Fever | 6 | 8 | 34
Abdominal Pain | 5 | 6 | 18
Neutropenia | 4 | 3 | 16
Coughing | 3 | 4 | 25
Fatigue | 3 | 5 | 13
Herpes Simplex | 3 | 3 | 11
Pneumonia | 3 | 2 | 10
Rash | 3 | 4 | 15
Anemia | 2 | 2 | 14
Anorexia | 2 | 2 | 19
Asthenia | 2 | 2 | 13
Sweating Increased | 2 | 2 | 10
Candidiasis, Oral | 1 | <1 | 12
Dehydration | 1 | 3 | 11
Dyspnea | 1 | 3 | 12
Insomnia | 1 | 1 | 16
Pain | 1 | 1 | 11
Weight Decrease | 1 | <1 | 14
Rigors | <1 | 2 | 12
OPC=oropharyngeal candidiasis

Additional Adverse Reactions Reported in Less Than 5% of Noxafil-Treated Patients in Clinical Trials

Other clinically significant adverse reactions reported in less than 5% of patients in clinical trials of Noxafil are listed below:

- Blood and lymphatic system disorders: hemolytic uremic syndrome, thrombotic thrombocytopenic purpura, neutropenia aggravated
- Endocrine disorders: adrenal insufficiency
- Nervous system disorders: paresthesia
- Immune system disorders: allergic reaction [see Contraindications (4.1)]
- Cardiac disorders: torsades de pointes [see Warnings and Precautions (5.2)]
- Vascular disorders: pulmonary embolism
- Gastrointestinal disorders: pancreatitis
- Liver and Biliary System Disorders: hepatic enzymes increased, hepatic function abnormal, hepatitis, hepatomegaly, jaundice
- Renal & Urinary System Disorders: renal failure acute

Liver Test Abnormalities in the Clinical Trials of Noxafil Oral Suspension

Liver Test Abnormalities in the Clinical Trials with Noxafil Oral Suspension for Prophylaxis of Invasive Aspergillus and Candida Infections

In the prophylaxis of invasive Aspergillus and Candida infections studies, the number and percentage of patients with changes in liver tests from Common Toxicity Criteria (CTC) Grade 0, 1, or 2 at baseline to Grade 3 or 4 at the end of the studies is presented in Table 12.

Table 12: Changes in Liver Test Results from CTC Grade 0, 1, or 2 at Baseline to Grade 3 or 4 in Prophylaxis of Invasive Aspergillus and Candida Infections Studies (Noxafil Oral Suspension Studies 1 and 2)
Number (%) of Patients with Change [Change from Grade 0 to 2 at baseline to Grade 3 or 4 during the study. These data are presented in the form X/Y, where X represents the number of patients who met the criterion as indicated, and Y represents the number of patients who had a baseline observation and at least one post-baseline observation.]
Noxafil Oral Suspension Study 1
Noxafil Oral Suspension Study 1 | Laboratory Parameter | Noxafil Oral Suspension n=301 | Fluconazole n=299
Noxafil Oral Suspension Study 1 | AST | 11/266 (4) | 13/266 (5)
ALT | 47/271 (17) | 39/272 (14)
Bilirubin | 24/271 (9) | 20/275 (7)
Alkaline Phosphatase | 9/271 (3) | 8/271 (3)
Noxafil Oral Suspension Study 2
Laboratory Parameter | Noxafil Oral Suspension (n=304) | Fluconazole/Itraconazole (n=298)
AST | 9/286 (3) | 5/280 (2)
ALT | 18/289 (6) | 13/284 (5)
Bilirubin | 20/290 (7) | 25/285 (9)
Alkaline Phosphatase | 4/281 (1) | 1/276 (<1)
CTC = Common Toxicity Criteria; AST= Aspartate Aminotransferase;
ALT= Alanine Aminotransferase.

Liver Test Abnormalities in the Clinical Trials with Noxafil Oral Suspension for the Treatment of OPC

The number and percentage of patients treated for OPC with clinically significant liver test abnormalities at any time during the studies is provided in Table 13 (liver test abnormalities were present in some of these patients prior to initiation of the study drug).

Table 13: Clinically Significant Liver Test Abnormalities without Regard to Baseline Value (Noxafil Oral Suspension Studies for the Treatment of OPC)
Laboratory Test | Nonrefractory OPC |  | Refractory OPC
Laboratory Test | Noxafil Oral Suspension | Fluconazole | Noxafil Oral Suspension
Laboratory Test | n=557 (%) | n=262 (%) | n=239 (%)
ALT > 3.0 x ULN | 16/537 (3) | 13/254 (5) | 25/226 (11)
AST > 3.0 x ULN | 33/537 (6) | 26/254 (10) | 39/223 (17)
Total Bilirubin > 1.5 x ULN | 15/536 (3) | 5/254 (2) | 9/197 (5)
Alkaline Phosphatase > 3.0 x ULN | 17/535 (3) | 15/253 (6) | 24/190 (13)
ALT= Alanine Aminotransferase; AST= Aspartate Aminotransferase.

Liver Test Abnormalities in the Clinical Trials with Noxafil Oral Suspension for the Treatment of Invasive Aspergillosis

The number and percentage of patients treated for invasive aspergillosis with clinically significant liver test abnormalities at any time during the Aspergillosis Treatment Study is provided in Table 14. Liver test abnormalities present prior to the initiation of study drug included: ALT (22% of the patients), AST (13% of the patients), and bilirubin (13% of the patients).

Table 14: Changes in Liver Test Results from CTC Grade 0, 1, or 2 at Baseline to Grade 3 or 4 (Aspergillosis Treatment Study)
Number (%) of Patients with Change [Change from Grade 0 to 2 at baseline to Grade 3 or 4 during the study. These data are presented in the form n/N, where n represents the number of patients who met the criterion as indicated, and N represents the number of patients who had a baseline observation and at least one post-baseline observation.]
Laboratory Parameter | Noxafil n/N (%) | Voriconazole n/N (%)
AST | 22/281 (8) | 21/285 (7)
ALT | 29/281(10) | 23/282 (8)
Bilirubin | 26/280 (9) | 25/284 (9)
Alkaline Phosphatase | 12/282 (4) | 20/284 (7)
N=Number of patients for a given laboratory test with a baseline value of CTC Grade 0, 1, or 2 and at least one post-baseline value.
CTC = Common Toxicity Criteria; AST= Aspartate Aminotransferase;
ALT= Alanine Aminotransferase.

In healthy volunteers and patients, elevation of liver test values did not appear to be associated with higher plasma posaconazole concentrations.

Clinical Trials in Pediatric Patients 2 Years of Age and Older

The safety of Noxafil injection and Noxafil PowderMix (for delayed-release oral suspension) for prophylaxis of invasive fungal infections was evaluated in an open-label uncontrolled dose-ranging pharmacokinetic and safety study of Noxafil injection and Noxafil PowderMix (Pediatric Study 1, NCT02452034). In this study, 115 immunocompromised pediatric patients 2 to less than 18 years of age with known or expected neutropenia initially received Noxafil injection (up to 6 mg/kg twice daily for the first day and then up to 6 mg/kg for at least 7 days), and then 63 patients were transitioned to Noxafil PowderMix (up to 6 mg/kg once daily). The mean overall treatment duration was 21 days including a mean duration of 14 days (range: 1 to 28 days) on Noxafil injection and a mean duration of 12 days (range: 2 to 18 days) on Noxafil PowderMix [see Clinical Pharmacology (12.3)]. In this study, the reported adverse reaction profile of Noxafil injection and Noxafil PowderMix in pediatric patients was consistent with the safety profile of Noxafil in adults. The most common adverse reactions that occurred in greater than 20% of pediatric patients who received Noxafil injection and Noxafil PowderMix were pyrexia, febrile neutropenia, vomiting, mucosal inflammation, pruritus, hypertension, hypokalemia, and stomatitis.

The safety of Noxafil injection, Noxafil delayed-release tablets, and Noxafil PowderMix for delayed-release oral suspension for the treatment of invasive aspergillosis was evaluated in an open-label, non-comparative clinical study in 31 pediatric patients 2 to less than 18 years of age with a diagnosis of possible, probable, or proven invasive aspergillosis (Pediatric Study 2, NCT04218851). In this study, all 31 pediatric patients initially received Noxafil injection (6 mg/kg twice daily on the first day and then 6 mg/kg once daily) for the treatment of invasive aspergillosis; 12 patients were transitioned to Noxafil delayed-release tablets (300 mg once daily) if they weighed ≥40 kg, and 10 patients were transitioned to Noxafil PowderMix (based on weight) if they weighed 10 to 40 kg [see Dosage and Administration (2.3)]. The mean overall treatment duration was 50 days including 15 days (range: 2 to 78 days) on Noxafil injection, 54 days (range: 6 to 80 days) on Noxafil delayed-release tablets, and 44 days (range: 7 to 76 days) on Noxafil PowderMix. The reported adverse reaction profile of Noxafil injection, Noxafil delayed-release tablets, and Noxafil PowderMix in pediatric patients was consistent with the known safety profile of Noxafil in adults. The most common adverse reactions that occurred in greater than 20% of pediatric patients who received any of the three formulations of Noxafil were vomiting, pyrexia, abdominal pain, liver test abnormalities, and hypertension.

6.2 Postmarketing Experience

The following adverse reaction has been identified during the post-approval use of Noxafil. Because these reactions are reported voluntarily from a population of uncertain size, it is not always possible to reliably estimate their frequency or establish a causal relationship to drug exposure.

Endocrine Disorders: Pseudoaldosteronism

7 DRUG INTERACTIONS

Table 15 and Table 17 include drugs with clinically important drug interactions when administered concomitantly with Noxafil and Noxafil PowderMix and instructions for preventing or managing them. Table 16 includes important drug interactions specific to the absorption of posaconazole administered as either Noxafil oral suspension or Noxafil PowderMix.

These recommendations are based on either drug interaction studies or predicted interactions due to the expected magnitude of interaction and potential for serious adverse reactions or loss of efficacy [see Clinical Pharmacology (12.3)].

The following information was derived from data with Noxafil oral suspension or another posaconazole tablet formulation unless otherwise noted. All clinically important drug interactions with Noxafil oral suspension, except for those that affect the absorption of posaconazole (via gastric pH and motility), are considered relevant to clinically important drug interactions with Noxafil injection, Noxafil delayed-release tablets, and Noxafil PowderMix for delayed-release oral suspension [see Clinical Pharmacology (12.3)].

Consult the labeling of concomitantly used drugs to obtain further information about interactions with posaconazole.

7.1 Effects of Other Drugs on Noxafil and Noxafil PowderMix

Posaconazole is primarily metabolized via UDP-glucuronosyltransferase and is a substrate of p-glycoprotein (P-gp) efflux. Therefore, inhibitors or inducers of these clearance pathways may affect posaconazole plasma concentrations. Concomitant use of Noxafil with drugs that can decrease the plasma posaconazole concentrations should generally be avoided unless the benefit outweighs the risk. If such drugs are necessary, patients should be monitored closely for breakthrough fungal infections.

Table 15: Drug Interactions Affecting Noxafil and Noxafil PowderMix When Administered Concomitantly with Other Drugs
UDP-Glucuronidase Inducers
Mechanism and Clinical Effect(s) | Posaconazole is a UDP-glucuronosyltransferase substrate. Concomitant use of Noxafil with UDP-glucuronidase inducers may decrease posaconazole exposure [see Clinical Pharmacology (12.3)], which may reduce the effectiveness of posaconazole.
Prevention or Management | Efavirenz | Avoid concomitant use of posaconazole with efavirenz, unless the benefit outweighs the risks.
Prevention or Management | Rifabutin | Avoid concomitant use of posaconazole with rifabutin unless the benefit to the patient outweighs the risk. If concomitant use is needed, monitor closely for breakthrough fungal infections. See Table 17 for rifabutin monitoring considerations when posaconazole affects rifabutin via CYP3A4 inhibition.
Prevention or Management | Phenytoin | Avoid concomitant use of posaconazole with phenytoin unless the benefit to the patient outweighs the risk. If concomitant use is needed, monitor for breakthrough fungal infections. See Table 17 for phenytoin monitoring considerations when posaconazole affects phenytoin via CYP3A4 inhibition.
Fosamprenavir
Mechanism and Clinical Effect(s) | Concomitant use of Noxafil with fosamprenavir may lead to decreased posaconazole plasma concentrations [see Clinical Pharmacology (12.3)], which may reduce effectiveness of posaconazole.
Prevention or Management | If concomitant use of posaconazole with fosamprenavir is needed, monitor closely for breakthrough fungal infections.

Table 16: Drug Interactions Affecting Noxafil Oral Suspension and Noxafil PowderMix Absorption When Administered Concomitantly with Other Drugs
Noxafil Oral Suspension
Cimetidine and Esomeprazole
Mechanism and Clinical Effect(s) | Concomitant use of Noxafil oral suspension with cimetidine or esomeprazole resulted in decreased posaconazole plasma concentrations [see Clinical Pharmacology (12.3)], which may reduce effectiveness of Noxafil.
Prevention or Management | Avoid concomitant use of Noxafil oral suspension with cimetidine or esomeprazole unless the benefit outweighs the risks. If concomitant use is needed, monitor closely for breakthrough fungal infections.
Metoclopramide
Mechanism and Clinical Effect(s) | Concomitant use of Noxafil oral suspension with metoclopramide decreased posaconazole plasma concentrations [see Clinical Pharmacology (12.3)], which may reduce effectiveness of Noxafil oral suspension.
Prevention or Management | If Noxafil oral suspension is concomitantly administered with metoclopramide, closely monitor for breakthrough fungal infections.
Noxafil Oral PowderMix
Alcohol
Mechanism and Clinical Effect(s) | Posaconazole releases faster from Noxafil PowderMix in the presence of alcohol, which may interfere with Noxafil PowderMix’s delayed-release characteristics [see Clinical Pharmacology (12.3)].
Prevention or Management | Administration of Noxafil PowderMix with alcohol is not recommended.

7.2 Effects of Noxafil and Noxafil PowderMix on Other Drugs

Posaconazole is a strong CYP3A4 inhibitor. Therefore, concomitant use of Noxafil may increase plasma concentrations of drugs that are CYP3A4 substrates [see Clinical Pharmacology (12.3)].

Table 17: Drug Interactions Affecting Drugs Administered Concomitantly with Noxafil and Noxafil PowderMix
Digoxin
Clinical Effect(s) | Increased digoxin plasma concentrations have been reported in patients who received concomitant posaconazole and digoxin.
Prevention or Management | Monitor digoxin plasma concentrations during concomitant use of posaconazole.
Glipizide
Clinical Effect(s) | No dosage modification of glipizide is needed when used concomitantly with Noxafil. However, glucose concentrations decrease in some patients concomitantly administered posaconazole and glipizide.
Prevention or Management | Increase monitoring of glucose concentrations when used concomitantly.
CYP3A Substrates
Immunosuppressants that are CYP3A4 Substrates
Mechanism and Clinical Effect(s) | Posaconazole is a strong CYP3A4 inhibitor. Therefore, plasma concentrations of CYP3A4 substrates may be increased by posaconazole use [see Clinical Pharmacology (12.3)].
Prevention or Management | Sirolimus | Posaconazole is contraindicated with sirolimus [see Clinical Pharmacology (12.3)].
Prevention or Management | Tacrolimus | • At initiation of posaconazole treatment, reduce the tacrolimus dosage to approximately one-third of the original tacrolimus dosage. • Frequent monitoring of tacrolimus whole blood trough concentrations should be performed during and at discontinuation of posaconazole treatment and the tacrolimus dosage should be modified accordingly [see Warnings and Precautions (5.1) and Clinical Pharmacology (12.3)].
Prevention or Management | Cyclosporine | • At initiation of posaconazole treatment reduce the cyclosporine dosage to approximately three-fourths of the original dosage. • Frequent monitoring of cyclosporine whole blood trough concentrations should be performed during and at discontinuation of posaconazole treatment and the cyclosporine dosage should be modified accordingly [see Warnings and Precautions (5.1) and Clinical Pharmacology (12.3)].
CYP3A4 Substrates that Prolong QTc Interval
Mechanism and Clinical Effect(s) | Concomitant use of posaconazole with CYP3A4 substrates such as pimozide and quinidine may result in increased plasma concentrations of the CYP3A4 substrates leading to QTc interval prolongation and torsades de pointes [see Warnings and Precautions (5.2)].
Prevention or Management | Pimozide | Concomitant use with posaconazole is contraindicated.
Prevention or Management | Quinidine | Concomitant use with posaconazole is contraindicated.
HMG-CoA Reductase Inhibitors (Statins) that are CYP3A4 Substrates
Mechanism and Clinical Effect(s) | Concomitant use of posaconazole with simvastatin increased simvastatin plasma concentrations which can lead to rhabdomyolysis [see Clinical Pharmacology (12.3)].
Prevention or Management | Atorvastatin, Lovastatin, Simvastatin | Concomitant use with posaconazole is contraindicated.
Benzodiazepines that are CYP3A4 Substrates
Mechanism and Clinical Effect(s) | Concomitant use of posaconazole with midazolam increased midazolam plasma concentrations which could potentiate and prolong hypnotic and sedative effects [see Clinical Pharmacology (12.3)].
Prevention or Management | Midazolam, Alprazolam, Triazolam | Closely monitor for adverse reactions associated with high plasma concentrations of benzodiazepines that are CYP3A4 substrates during concomitant use, and a benzodiazepine receptor antagonist should be available to reverse effects [see Warnings and Precautions (5.7)].
Calcium Channel Blockers that are CYP3A4 Substrates
Mechanism and Clinical Effect(s) | Posaconazole may increase the plasma concentrations of calcium channel blockers that are substrates of CYP3A4.
Prevention or Management | Verapamil, Diltiazem, Nifedipine, Nicardipine, Felodipine | Monitor frequently for adverse reactions and toxicity with concomitant use of posaconazole with calcium channel blockers that are CYP3A4 substrates. Dosage reduction of the calcium channel blocker may be needed.
Anti-HIV Drugs that are CYP3A4 Substrates
Mechanism and Clinical Effect(s) | Ritonavir and atazanavir are CYP3A4 substrates and posaconazole increased plasma concentrations of these drugs [see Clinical Pharmacology (12.3)].
Prevention or Management | Ritonavir and Atazanavir | Monitor frequently for adverse reactions and toxicity of ritonavir and atazanavir during concomitant use.
Antineoplastic Drugs that are CYP3A4 Substrates
Mechanism and Clinical Effect(s) | Posaconazole may increase plasma concentrations of oncology drugs that are CYP3A4 substrates, which may increase the risk of serious adverse reactions.
Prevention or Management | Venetoclax | CLL/SLL patients: Concomitant use of posaconazole with venetoclax during initiation and ramp-up phase is contraindicated. AML patients: With concomitant use, venetoclax dosage reduction and safety monitoring is recommended across all dosing phases [see Warnings and Precautions (5.11)].
Prevention or Management | Vinca alkaloids (e.g., vincristine, vinblastine) | Reserve concomitant use for patients with no alternative antifungal treatment options [see Warnings and Precautions (5.8)].
Ergot Alkaloids
Mechanism and Clinical Effect(s) | Most of the ergot alkaloids are CYP3A4 substrates. Posaconazole may increase the plasma concentrations of ergot alkaloids (ergotamine and dihydroergotamine) which may lead to ergotism.
Prevention or Management | Ergotamine, Dihydroergotamine | Concomitant use with posaconazole is contraindicated.
Phenytoin
Mechanism and Clinical Effect(s) | Phenytoin is a CYP3A4 substrate. Concomitant use of posaconazole with phenytoin increased phenytoin plasma concentrations [see Clinical Pharmacology (12.3)].
Prevention or Management | Avoid concomitant use of posaconazole with phenytoin unless the benefit outweighs the risk. frequently monitor phenytoin concentrations and consider a dosage reduction of phenytoin. See Table 15 for additional monitoring considerations when phenytoin affects posaconazole via UDP-glucuronosyltransferase inhibition.
Rifabutin
Mechanism and Clinical Effect(s) | Rifabutin is a CYP3A4 substrate. Concomitant use of posaconazole with rifabutin increased rifabutin plasma concentrations [see Clinical Pharmacology (12.3)].
Prevention or Management | Avoid concomitant use of posaconazole with rifabutin unless the benefit outweighs the risk. Frequent monitoring of full blood counts and adverse reactions due to increased rifabutin plasma concentrations (e.g., uveitis, leukopenia) during concomitant use are recommended. See Table 15 for additional monitoring considerations when rifabutin affects posaconazole via UDP-glucuronosyltransferase inhibition.

7.3 Absence of Clinically Important Interaction with Noxafil and Noxafil PowderMix

Additional clinical studies demonstrated that no clinically important effects on zidovudine, lamivudine, indinavir, or caffeine were observed when administered with Noxafil 200 mg once daily; therefore, no dose adjustments are required for these drugs when coadministered with Noxafil 200 mg once daily.

No clinically relevant effects on the pharmacokinetics of Noxafil delayed-release tablets were observed during concomitant use with antacids, H2-receptor antagonists and proton pump inhibitors, and metoclopramide [see Clinical Pharmacology (12.3)]. No dosage adjustment of Noxafil delayed-release tablets or Noxafil PowderMix for delayed-release oral suspension is required during concomitant use with these drugs.

No clinically relevant effects on the pharmacokinetics of Noxafil oral suspension were observed during concomitant use with antacids, H2-receptor antagonists (other than cimetidine), and loperamide [see Clinical Pharmacology (12.3)]. No dosage adjustment of Noxafil oral suspension is required during concomitant use with these drugs (other than cimetidine).

8 USE IN SPECIFIC POPULATIONS

8.1 Pregnancy

Risk Summary

Based on findings from animal data, Noxafil may cause fetal harm when administered to pregnant women. Available data for use of Noxafil in pregnant women are insufficient to establish a drug-associated risk of major birth defects, miscarriage, or adverse maternal or fetal outcomes. In animal reproduction studies, skeletal malformations were observed when posaconazole was dosed orally to pregnant rats during organogenesis at doses ≥1.4 times the 400 mg twice daily oral suspension regimen based on steady-state plasma concentrations of Noxafil in healthy volunteers. In pregnant rabbits dosed orally during organogenesis, doses of ≥ 3 times the clinical exposure caused an increase in resorptions (see Data). Based on animal data, advise pregnant women of the potential risk to a fetus.

The estimated background risk of major birth defects and miscarriage for the indicated populations is unknown. All pregnancies have a background risk of birth defect, loss, or other adverse outcomes. In the U.S. general population, the estimated background risk of major birth defects and miscarriage in clinically recognized pregnancies is 2 to 4% and 15 to 20%, respectively.

Data

Animal Data: Posaconazole resulted in maternal toxicity (reduced food consumption and reduced body weight gain) and skeletal malformations (cranial malformations and missing ribs) when given orally to pregnant rats during organogenesis (Gestational Days 6 through 15) at doses ≥27 mg/kg (≥1.4 times the 400 mg twice daily oral suspension regimen based on steady-state plasma concentrations of drug in healthy volunteers). The no-effect dose for malformations and maternal toxicity in rats was 9 mg/kg, which is 0.7 times the exposure achieved with the 400 mg twice daily oral suspension regimen. No malformations were seen in rabbits dosed during organogenesis (Gestational Days 7 through 19) at doses up to 80 mg/kg (5 times the exposure achieved with the 400 mg twice daily oral suspension regimen). In the rabbit, the no-effect dose was 20 mg/kg, while high doses of 40 mg/kg and 80 mg/kg (3 or 5 times the clinical exposure) caused an increase in resorptions. In rabbits dosed at 80 mg/kg, a reduction in body weight gain of females and a reduction in litter size were seen.

8.2 Lactation

Risk Summary

There are no data on the presence of posaconazole in human milk, the effects on the breastfed infant, or the effects on milk production. Posaconazole is excreted in the milk of lactating rats. When a drug is present in animal milk, it is likely that the drug will be present in human milk. The developmental and health benefits of breastfeeding should be considered along with the mother’s clinical need for Noxafil and any potential adverse effects on the breastfed child from Noxafil or from the underlying maternal condition.

8.4 Pediatric Use

The three Noxafil dosage forms (injection, delayed-release tablets, oral suspension) and one Noxafil PowderMix (for delayed-release oral suspension) dosage form are different products; are approved for different pediatric indications, age groups, and weights; have different dosing regimens; and have different preparation and administration instructions. Therefore, select the recommended dosage form based on the pediatric indication, age group, and weight [see Dosage and Administration (2.1)].

Noxafil PowderMix for delayed-release oral suspension is contraindicated in patients with HFI. Because a diagnosis of HFI may not yet be established in pediatric patients, obtain a careful history of HFI symptoms with sorbitol/fructose/sucrose exposure prior to administration of Noxafil PowderMix for delayed-release oral suspension [see Warnings and Precautions (5.9)].

Treatment of Invasive Aspergillosis

The safety and effectiveness of Noxafil (injection and delayed-release tablets) have been established for the treatment of invasive aspergillosis in pediatric patients 2 years of age and older .

The safety and effectiveness of Noxafil PowderMix have been established for the treatment of invasive aspergillosis in pediatric patients 2 years of age and older who weigh 10 kg to 40 kg.

Use of Noxafil and Noxafil PowderMix for these pediatric indications is supported by evidence from adequate and well-controlled studies of Noxafil in adults and safety and pharmacokinetic (PK) data from two pediatric studies [see Adverse Reactions (6.1) and Clinical Pharmacology (12.3)]. The safety of Noxafil and Noxafil PowderMix in pediatric patients for these pediatric indications was consistent with the known safety profile of Noxafil in adults [see Adverse Reactions (6.1)].

Noxafil PowderMix for delayed-release oral suspension is not recommended for use in patients who weigh greater than 40 kg because the recommended dosage cannot be achieved with this dosage form.

The safety and effectiveness of Noxafil and Noxafil PowderMix have not been established in pediatric patients less than 2 years of age.

Prophylaxis of Invasive Aspergillus and Candida Infections

The safety and effectiveness of Noxafil (injection and delayed-release tablets) have been established for the prophylaxis of invasive Aspergillus and Candida infections in pediatric patients 2 years of age and older who are at high risk of developing these infections due to being severely immunocompromised.

The safety and effectiveness of Noxafil oral suspension have been established for the prophylaxis of invasive Aspergillus and Candida infections in pediatric patients 13 years of age and older who are at high risk of developing these infections due to being severely immunocompromised.

The safety and effectiveness of Noxafil PowderMix have been established for the prophylaxis of invasive Aspergillus and Candida infections in pediatric patients 2 years of age and older who weigh 10 kg to 40 kg who are at high risk of developing these infections due to being severely immunocompromised.

Use of Noxafil and Noxafil PowderMix for these pediatric indications is supported by adequate and well controlled studies of Noxafil in adults and pediatric patients aged 13 years of age and older and additional PK and safety data in pediatric patients 2 years of age and older [see Clinical Pharmacology (12.3) and Clinical studies (14)].

Noxafil PowderMix is not recommended for use in patients who weigh greater than 40 kg because the recommended dosage cannot be achieved with this dosage form.

The safety and effectiveness of Noxafil and Noxafil PowderMix have not been established in pediatric patients less than 2 years of age.

Treatment of Oropharyngeal Candidiasis, including Refractory to Itraconazole and/or Fluconazole

The safety and effectiveness of Noxafil oral suspension have been established for the treatment of oropharyngeal candidiasis (OPC), including OPC refractory (rOPC) to itraconazole and/or fluconazole in pediatric patients 13 years of age and older.

Use of Noxafil oral suspension for this pediatric indication is supported by adequate and well controlled studies in adults and pediatric patients 13 years of age and older [see Clinical studies (14.4)].

The Noxafil injection, Noxafil delayed-release tablets, and Noxafil PowderMix products are not approved for the treatment of oropharyngeal candidiasis in pediatric patients. Noxafil Oral Suspension is the only dosage form approved for the treatment of OPC and rOPC in pediatric patients [see Dosage and Administration (2.4)].

The safety and effectiveness of Noxafil oral suspension for the treatment of OPC and rOPC have not been established in pediatric patients less than 13 years of age.

8.5 Geriatric Use

No overall differences in the safety or effectiveness of Noxafil injection, Noxafil delayed-release tablets, and Noxafil oral suspension have been observed between geriatric patients and younger adult patients in the clinical trials; therefore, the recommended dosage in geriatric patients is the same as that for younger adult patients. No clinically meaningful differences in posaconazole pharmacokinetics were observed in Noxafil-treated geriatric patients compared to Noxafil-treated younger adult patients during clinical trials [see Clinical Pharmacology (12.3)].

- Of the 279 patients treated with Noxafil injection in the Noxafil Injection Study (prophylaxis of invasive Aspergillus and Candida infections in those at high risk of developing these infections due to being severely immunocompromised), 52 (19%) patients were >65 years of age.
- Of the 230 patients treated with Noxafil delayed-release tablets, 38 (17%) patients were >65 years of age.
- Of the 605 patients treated with Noxafil oral suspension in Noxafil Oral Suspension Study 1 and Study 2 (prophylaxis of invasive Aspergillus and Candida infections in those at high risk of developing these infections due to being severely immunocompromised), 63 (10%) patients were ≥65 years of age.
- In studies of Noxafil for an unapproved indication, 48 patients treated with Noxafil oral suspension (greater than or equal to 800 mg/day (eight times the maximum recommended maintenance dosage for the treatment of OPC)) were ≥65 years of age.
- Of the 288 patients treated with Noxafil injection or Noxafil delayed-release tablets in the Aspergillosis Treatment Study, 85 (29%) patients were ≥65 years of age.

8.6 Renal Impairment

Noxafil Oral Suspension and Noxafil Delayed-Release Tablets

No dosage adjustment is required for patients with eGFR 20 mL/minute/1.73 m^2 or higher.
Due to variability in posaconazole exposure, closely monitor patients with eGFR less than 20 mL/minute/1.73 m^2 for breakthrough fungal infections. [see Clinical Pharmacology (12.3)].

Noxafil Injection

Avoid use of Noxafil injection in patients with eGFR less than 50 mL/minute/1.73 m^2 unless the benefit/risk to the patient justifies its use. The inactive ingredient in Noxafil injection, Betadex Sulfobutyl Ether Sodium (SBECD) is expected to accumulate in patients with reduced renal function. Safety and effectiveness of Noxafil injection have not been established in patients with less than 50 mL/minute/1.73 m^2.

If treatment with Noxafil injection is unavoidable in patients with eGFR less than 50 mL/minute/1.73 m^2, monitor serum creatinine levels. If serum creatinine increases, consider changing to oral Noxafil therapy.

8.7 Hepatic Impairment

No dosage adjustment is recommended for Noxafil oral suspension, Noxafil delayed-release tablets, Noxafil PowderMix for delayed-release oral suspension, and Noxafil injection in patients with mild, moderate, or severe hepatic impairment (Child-Pugh Class A, B, or C, respectively) [see Clinical Pharmacology (12.3)].

However, a specific hepatic impairment study has not been conducted with the Noxafil delayed-release tablets, Noxafil PowderMix for delayed-release oral suspension, or Noxafil injection.

8.8 Sex

No adjustment in the dosage of Noxafil is necessary based on sex.

8.9 Race

No adjustment in the dosage of Noxafil is necessary based on race.

8.10 Weight

Pharmacokinetic modeling suggests that patients who weigh greater than 120 kg may have lower posaconazole plasma drug exposure. Therefore, consider closely monitoring for breakthrough fungal infections particularly when using Noxafil oral suspension in patients weighing greater than 120 kg [see Clinical Pharmacology (12.3)].

10 OVERDOSAGE

There is no experience with overdosage of Noxafil injection and Noxafil delayed-release tablets.

During the clinical trials, some patients received Noxafil oral suspension up to 1,600 mg/day with no adverse reactions noted that were different from the lower doses. In addition, accidental overdose was noted in one patient who took 1200 mg twice daily Noxafil oral suspension for 3 days. No related adverse reactions were noted by the investigator.

Posaconazole is not removed by hemodialysis.

11 DESCRIPTION

Noxafil and Noxafil PowderMix contain posaconazole, an azole antifungal agent.

Posaconazole is designated chemically as 4-[4-[4-[4-[[ (3R,5R)-5- (2,4-difluorophenyl)tetrahydro-5- (1H-1,2,4-triazol-1-ylmethyl)-3-furanyl]methoxy]phenyl]-1-piperazinyl]phenyl]-2-[(1S,2S)-1-ethyl-2-hydroxypropyl]-2,4-dihydro-3H-1,2,4-triazol-3-one with an empirical formula of C37H42F2N8O4 and a molecular weight of 700.8. The chemical structure is:

Posaconazole is a white powder with a low aqueous solubility.

Noxafil (posaconazole) Injection

Noxafil injection, for intravenous use, is a clear colorless to yellow, without preservatives sterile liquid essentially free of foreign matter. Each vial contains 300 mg of posaconazole and the following inactive ingredients: 6.68 g Betadex Sulfobutyl Ether Sodium (SBECD), 0.0033 g edetate disodium, hydrochloric acid and sodium hydroxide to adjust the pH to 2.6, and water for injection.

Noxafil (posaconazole) Delayed-Release Tablets

Noxafil delayed-release tablet, for oral use, is yellow, coated, and oblong and contains 100 mg of posaconazole. Each delayed-release tablet contains the following inactive ingredients: croscarmellose sodium, hydroxypropylcellulose, hypromellose acetate succinate, iron oxide yellow, Macrogol/PEG 3350, magnesium stearate, microcrystalline cellulose, polyvinyl alcohol partially hydrolyzed, silicon dioxide, talc, and titanium dioxide.

Noxafil (posaconazole) Oral Suspension

Noxafil oral suspension is a white, cherry-flavored immediate-release suspension that contains 40 mg of posaconazole per mL and the following inactive ingredients: artificial cherry flavor, citric acid monohydrate, glycerin, liquid glucose, polysorbate 80, purified water, simethicone, sodium benzoate, sodium citrate dihydrate, titanium dioxide, and xanthan gum.

Noxafil PowderMix (posaconazole) for Delayed-Release Oral Suspension

Noxafil PowderMix for delayed-release oral suspension is supplied as a component of a kit. Each kit contains Noxafil as an off-white to yellowish powder for delayed-release oral suspension, a bottle of mixing liquid, two 3 mL (green) notched tip syringes, two 10 mL (blue) notched tip syringes, two mixing cups, and one bottle adapter for the mixing liquid bottle.

- Noxafil PowderMix for delayed-release oral suspension contains 300 mg of posaconazole and the following inactive ingredient: hypromellose acetate succinate.
- The mixing liquid contains: anhydrous citric acid, antifoam Af emulsion, berry citrus sweet flavor, carboxymethylcellulose sodium, carrageenan calcium sulfate trisodium phosphate, glycerin, methylparaben, microcrystalline cellulose, potassium sorbate, propylparaben, purified water, sodium citrate, sodium phosphate monobasic monohydrate, sodium saccharin, sorbitol solution, and xanthan gum.

12 CLINICAL PHARMACOLOGY

12.1 Mechanism of Action

Posaconazole is an azole antifungal agent [see Clinical Pharmacology (12.4)].

12.2 Pharmacodynamics

Exposure Response Relationship: Prophylaxis of invasive Aspergillus and Candida Infections in Adults Who Are at High Risk of Developing These Infections Due to Being Severely Immunocompromised

In clinical studies of neutropenic patients who were receiving cytotoxic chemotherapy for acute myelogenous leukemia (AML) or myelodysplastic syndromes (MDS) or hematopoietic stem cell transplant (HSCT) recipients with Graft versus Host Disease (GVHD), a wide range of plasma posaconazole exposures was noted following administration of Noxafil oral suspension. A pharmacokinetic-pharmacodynamic analysis of patient data revealed an apparent association between average posaconazole concentrations (Cavg) and prophylactic efficacy (Table 18). A lower Cavg may be associated with an increased risk of treatment failure, defined as treatment discontinuation, use of empiric systemic antifungal therapy (SAF), or occurrence of breakthrough invasive fungal infections.

Table 18: Noxafil Oral Suspension Exposure Analysis (Cavg) in Prophylaxis Trials
 | Prophylaxis in AML/MDS [Neutropenic patients who were receiving cytotoxic chemotherapy for AML or MDS] |  | Prophylaxis in GVHD [HSCT recipients with GVHD]
 | Cavg Range (ng/mL) | Treatment Failure [Defined as treatment discontinuation, use of empiric systemic antifungal therapy (SAF), or occurrence of breakthrough invasive fungal infections] (%) | Cavg Range (ng/mL) | Treatment Failure (%)
Quartile 1 | 90-322 | 54.7 | 22-557 | 44.4
Quartile 2 | 322-490 | 37.0 | 557-915 | 20.6
Quartile 3 | 490-734 | 46.8 | 915-1563 | 17.5
Quartile 4 | 734-2200 | 27.8 | 1563-3650 | 17.5
Cavg = the average posaconazole concentration when measured at steady state

Exposure Response Relationship: Treatment of Invasive Aspergillosis in Adult and Adolescent Patients:

Across a range of posaconazole plasma minimum concentrations (Cmin, range: 244 to 5663 ng/mL) following administration of Noxafil injection and Noxafil delayed-release tablets in adult and pediatric patients aged 14 years and older treated for invasive aspergillosis in Aspergillosis Treatment Study, there was no association between posaconazole Cmin and treatment efficacy [see Clinical Pharmacology (12.3) and Clinical Studies (14.1)]. Similarly, across a range of population pharmacokinetic model-predicted steady-state plasma average concentrations (Cavg, range: 589 to 6315 ng/mL), there was no association between posaconazole Cavg and treatment efficacy.

12.3 Pharmacokinetics

General Pharmacokinetic Characteristics

General Pharmacokinetic Characteristics of Noxafil Injection

Noxafil injection exhibits dose proportional pharmacokinetics after single doses between 200 and 300 mg in healthy volunteers and patients. The mean pharmacokinetic parameters after single doses with Noxafil injection in healthy volunteers and patients are shown in Table 19.

Table 19: Summary of Mean Pharmacokinetic Parameters (%CV) in Healthy Volunteers (30 minute infusion via peripheral venous line) and Patients (90 minute infusion via central venous line) after Dosing with Noxafil Injection on Day 1
 | Dose (mg) | n | AUC0-∞ (ng∙hr/mL) | AUC0-12 (ng∙hr/mL) | Cmax (ng/mL) | t1/2 (hr) | CL (L/hr)
Healthy Volunteers | 200 | 9 | 35400 (50) | 8840 (20) | 2250 (29) | 23.6 (23) | 6.5 (32)
Healthy Volunteers | 300 | 9 | 46400 (26) | 13000 (13) | 2840 (30) | 24.6 (20) | 6.9 (27)
Patients | 200 | 30 | N/D | 5570 (32) | 954 (44) | N/D | N/D
Patients | 300 | 22 | N/D | 8240 (26) | 1590 (62) | N/D | N/D
AUC0-∞ = Area under the plasma concentration-time curve from time zero to infinity; AUC0-12 = Area under the plasma concentration-time curve from time zero to 12 hr after the first dose on Day 1; Cmax = maximum observed concentration; t½ = terminal phase half-life; CL = total body clearance; N/D = Not Determined

Table 20 displays the pharmacokinetic parameters of posaconazole in patients following administration of Noxafil injection 300 mg taken once a day for 10 or 14 days following twice daily dosing on Day 1.

Table 20: Arithmetic Mean (%CV) of PK Parameters in Serial PK-Evaluable Patients Following Dosing of Noxafil Injection (300 mg) [300 mg dose administered over 90 minutes once a day following twice daily dosing on Day 1]
Day | N | Cmax (ng/mL) | Tmax [Median (minimum-maximum)] (hr) | AUC0-24 (ng*hr/mL) | Cav (ng/mL) | Cmin (ng/mL)
10/14 | 49 | 3280 (74) | 1.5 (0.98-4.0) | 36100 (35) | 1500 (35) | 1090 (44)
AUC0-24 = area under the concentration-time curve over the dosing interval (i.e., 24 hours); Cav= time-averaged concentrations (i.e., AUC0-24h/24hr);
Cmin = POS trough level immediately before a subject received the dose of POS on the day specified in the protocol; Cmax = observed maximum plasma concentration; CV = coefficient of variation, expressed as a percent (%); Day = study day on treatment; Tmax = time of observed maximum plasma concentration.

General Pharmacokinetic Characteristics of Noxafil Delayed-Release Tablets

Noxafil delayed-release tablets exhibit dose proportional pharmacokinetics after single and multiple dosing up to 300 mg. The mean pharmacokinetic parameters of posaconazole at steady state following administration of Noxafil delayed-release tablets 300 mg twice daily on Day 1, then 300 mg once daily thereafter in healthy volunteers and in neutropenic patients who are receiving cytotoxic chemotherapy for AML or MDS or HSCT recipients with GVHD are shown in Table 21.

Table 21: Arithmetic Mean (%CV) of Steady State PK Parameters in Healthy Volunteers and Patients Following Administration of Noxafil Delayed-Release Tablets (300 mg) [300 mg twice daily on Day 1, then 300 mg once daily thereafter]
 | N | AUC0-24 hr (ng∙hr/mL) | Cav [Cav = time-averaged concentrations (i.e., AUC0-24 hr/24 hr)] (ng/mL) | Cmax (ng/mL) | Cmin (ng/mL) | Tmax [Median (minimum-maximum)] (hr) | t1/2 (hr) | CL/F (L/hr)
Healthy Volunteers | 12 | 51618 (25) | 2151 (25) | 2764 (21) | 1785 (29) | 4 (3-6) | 31 (40) | 7.5 (26)
Patients | 50 | 37900 (42) | 1580 (42) | 2090 (38) | 1310 (50) | 4 (1.3-8.3) | - | 9.39 (45)
CV = coefficient of variation expressed as a percentage (%CV); AUC0-T = Area under the plasma concentration-time curve from time zero to 24 hr; Cmax = maximum observed concentration; Cmin = minimum observed plasma concentration; Tmax = time of maximum observed concentration; t½ = terminal phase half-life; CL/F = Apparent total body clearance

General Pharmacokinetic Characteristics of Noxafil Oral Suspension

Dose-proportional increases in plasma exposure (AUC) to Noxafil oral suspension were observed following single oral doses from 50 mg to 800 mg and following multiple-dose administration from 50 mg twice daily to 400 mg twice daily in healthy volunteers. No further increases in exposure were observed when the dose of the oral suspension increased from 400 mg twice daily to 600 mg twice daily in febrile neutropenic patients or those with refractory invasive fungal infections.

The mean (%CV) [min-max] Noxafil oral suspension average steady-state plasma concentrations (Cavg) and steady-state pharmacokinetic parameters in patients following administration of 200 mg three times a day and 400 mg twice daily of the oral suspension are provided in Table 22.

Table 22: The Mean (%CV) [min-max] Posaconazole Steady-State Pharmacokinetic Parameters in Patients Following Oral Administration of Noxafil Oral Suspension 200 mg Three Times a Day and 400 mg Twice Daily
Dose [Oral suspension administration] | Cavg (ng/mL) | AUC [AUC (0-24 hr) for 200 mg three times a day and AUC (0-12 hr) for 400 mg twice daily] (ng∙hr/mL) | CL/F (L/hr) | V/F (L) | t½ (hr)
200 mg three times a day [HSCT recipients with GVHD] (n=252) | 1103 (67) [21.5-3650] | ND [Not done] | ND | ND | ND
200 mg three times a day [Neutropenic patients who were receiving cytotoxic chemotherapy for acute myelogenous leukemia or myelodysplastic syndromes] (n=215) | 583 (65) [89.7-2200] | 15,900 (62) [4100-56,100] | 51.2 (54) [10.7-146] | 2425 (39) [828-5702] | 37.2 (39) [19.1-148]
400 mg twice daily [Febrile neutropenic patients or patients with refractory invasive fungal infections, Cavg n=24] (n=23) | 723 (86) [6.70-2256] | 9093 (80) [1564-26,794] | 76.1 (78) [14.9-256] | 3088 (84) [407-13,140] | 31.7 (42) [12.4-67.3]
Cavg = the average posaconazole concentration when measured at steady state
The variability in average plasma posaconazole concentrations in patients was relatively higher than that in healthy subjects.

Absorption:

Absorption of Noxafil Delayed-Release Tablets

When given orally in healthy volunteers, Noxafil delayed-release tablets are absorbed with a median Tmax of 4 to 5 hours. Steady-state plasma concentrations are attained by Day 6 at the 300 mg dose (once daily after twice daily loading dose at Day 1). The absolute bioavailability of the oral delayed-release tablet is approximately 54% under fasted conditions. The Cmax and AUC of posaconazole following administration of Noxafil delayed-release tablets are increased 16% and 51%, respectively, when given with a high fat meal compared to a fasted state (see Table 23).

Table 23: Statistical Comparison of Plasma Pharmacokinetics of Posaconazole Following Single Oral Dose Administration of 300 mg Noxafil Delayed-Release Tablet to Healthy Subjects under Fasting and Fed Conditions
 | Fasting Conditions |  | Fed Conditions (High Fat Meal) [48.5 g fat] |  | Fed/Fasting
Pharmacokinetic Parameter | N | Mean (%CV) | N | Mean (%CV) | GMR (90% CI)
Cmax (ng/mL) | 14 | 935 (34) | 16 | 1060 (25) | 1.16 (0.96, 1.41)
AUC0-72hr (hr∙ng/mL) | 14 | 26200 (28) | 16 | 38400 (18) | 1.51 (1.33, 1.72)
Tmax [Median (Min, Max) reported for Tmax] (hr) | 14 | 5.00 (3.00, 8.00) | 16 | 6.00 (5.00, 24.00) | N/A
GMR=Geometric least-squares mean ratio; CI=Confidence interval

Absorption of Noxafil PowderMix for Delayed-Release Oral Suspension

The absolute bioavailability of the Noxafil PowderMix for delayed-release oral suspension is approximately 70-80%. The effect of food on the pharmacokinetics of the Noxafil PowderMix for delayed-release oral suspension has not been determined.

Absorption of Noxafil Oral Suspension

Noxafil oral suspension is absorbed with a median Tmax of ~3 to 5 hours. Steady-state plasma concentrations are attained at 7 to 10 days following multiple-dose administration.

Following single-dose administration of 200 mg, the mean AUC and Cmax of posaconazole are approximately 3 times higher when the oral suspension is administered with a nonfat meal and approximately 4 times higher when administered with a high-fat meal (~50 gm fat) relative to the fasted state. Following single-dose administration of Noxafil oral suspension 400 mg, the mean AUC and Cmax of posaconazole are approximately 3 times higher when administered with a liquid nutritional supplement (14 gm fat) relative to the fasted state (see Table 24). In addition, the effects of varying gastric administration conditions on the Cmax and AUC of Noxafil oral suspension in healthy volunteers have been investigated and are shown in Table 25.

To assure attainment of adequate plasma concentrations, it is recommended to administer Noxafil oral suspension during or immediately following a full meal. In patients who cannot eat a full meal, Noxafil oral suspension should be taken with a liquid nutritional supplement or an acidic carbonated beverage (e.g., ginger ale).

Table 24: The Mean (%CV) [min-max] Posaconazole Pharmacokinetic Parameters Following Single-Dose Noxafil Oral Suspension Administration of 200 mg and 400 mg Under Fed and Fasted Conditions
Dose (mg) | Cmax (ng/mL) | Tmax [Median [min-max].] (hr) | AUC (I) (ng∙hr/mL) | CL/F (L/hr) | t½ (hr)
200 mg fasted (n=20) [n=15 for AUC (I), CL/F, and t½] | 132 (50) [45-267] | 3.50 [1.5-36 [The subject with Tmax of 36 hrs had relatively constant plasma levels over 36 hrs (1.7 ng/mL difference between 4 hrs and 36 hrs).] ] | 4179 (31) [2705-7269] | 51 (25) [28-74] | 23.5 (25) [15.3-33.7]
200 mg nonfat (n=20) | 378 (43) [131-834] | 4 [3-5] | 10,753 (35) [4579-17,092] | 21 (39) [12-44] | 22.2 (18) [17.4-28.7]
200 mg high fat (54 gm fat) (n=20) | 512 (34) [241-1016] | 5 [4-5] | 15,059 (26) [10,341-24,476] | 14 (24) [8.2-19] | 23.0 (19) [17.2-33.4]
400 mg fasted (n=23) [n=10 for AUC (I), CL/F, and t½] | 121 (75) [27-366] | 4 [2-12] | 5258 (48) [2834-9567] | 91 (40) [42-141] | 27.3 (26) [16.8-38.9]
400 mg with liquid nutritional supplement (14 gm fat) (n=23) | 355 (43) [145-720] | 5 [4-8] | 11,295 (40) [3865-20,592] | 43 (56) [19-103] | 26.0 (19) [18.2-35.0]

Table 25: The Effect of Varying Gastric Administration Conditions on the Cmax and AUC of Noxafil Oral Suspension in Healthy Volunteers [In 5 subjects, the Cmax and AUC decreased substantially (range: -27% to -53% and -33% to -51%, respectively) when Noxafil was administered via an NG tube compared to when Noxafil was administered orally. It is recommended to closely monitor patients for breakthrough fungal infections when Noxafil is administered via an NG tube because a lower plasma exposure may be associated with an increased risk of treatment failure.]
Study Description | Administration Arms | Change in Cmax (ratio estimate [Ratio Estimate is the ratio of coadministered drug plus Noxafil to coadministered drug alone for Cmax or AUC.] ; 90% CI of the ratio estimate) | Change in AUC (ratio estimate; 90% CI of the ratio estimate)
400 mg single dose with a high-fat meal relative to fasted state (n=12) | 5 minutes before high-fat meal | ↑96% (1.96; 1.48-2.59) | ↑111% (2.11; 1.60-2.78)
400 mg single dose with a high-fat meal relative to fasted state (n=12) | During high-fat meal | ↑339% (4.39; 3.32-5.80) | ↑382% (4.82; 3.66-6.35)
400 mg single dose with a high-fat meal relative to fasted state (n=12) | 20 minutes after high-fat meal | ↑333% (4.33; 3.28-5.73) | ↑387% (4.87; 3.70-6.42)
400 mg twice daily and 200 mg four times daily for 7 days in fasted state and with liquid nutritional supplement (BOOST®) (n=12) | 400 mg twice daily with BOOST | ↑65% (1.65; 1.29-2.11) | ↑66% (1.66; 1.30-2.13)
400 mg twice daily and 200 mg four times daily for 7 days in fasted state and with liquid nutritional supplement (BOOST®) (n=12) | 200 mg four times daily with BOOST | No Effect | No Effect
Divided daily dose from 400 mg twice daily to 200 mg four times daily for 7 days regardless of fasted conditions or with BOOST (n=12) | Fasted state | ↑136% (2.36; 1.84-3.02) | ↑161% (2.61; 2.04-3.35)
Divided daily dose from 400 mg twice daily to 200 mg four times daily for 7 days regardless of fasted conditions or with BOOST (n=12) | With BOOST | ↑137% (2.37; 1.86-3.04) | ↑157% (2.57; 2.00-3.30)
400 mg single dose with carbonated acidic beverage (ginger ale) and/or proton pump inhibitor (esomeprazole) (n=12) | Ginger ale | ↑92% (1.92; 1.51-2.44) | ↑70% (1.70; 1.43-2.03)
400 mg single dose with carbonated acidic beverage (ginger ale) and/or proton pump inhibitor (esomeprazole) (n=12) | Esomeprazole | ↓32% (0.68; 0.53-0.86) | ↓30% (0.70; 0.59-0.83)
400 mg single dose with a prokinetic agent (metoclopramide 10 mg three times a day for 2 days) + BOOST or an antikinetic agent (loperamide 4 mg single dose) + BOOST (n=12) | With metoclopramide + BOOST | ↓21% (0.79; 0.72-0.87) | ↓19% (0.81; 0.72-0.91)
400 mg single dose with a prokinetic agent (metoclopramide 10 mg three times a day for 2 days) + BOOST or an antikinetic agent (loperamide 4 mg single dose) + BOOST (n=12) | With loperamide + BOOST | ↓3% (0.97; 0.88-1.07) | ↑11% (1.11; 0.99-1.25)
400 mg single dose either orally with BOOST or via an NG tube with BOOST (n=16) | Via NG tube [NG = nasogastric] | ↓19% (0.81; 0.71-0.91) | ↓23% (0.77; 0.69-0.86)

Distribution:

The mean volume of distribution of posaconazole after intravenous solution administration was 261 L and ranged from 226-295 L between studies and dose levels.

Posaconazole is highly bound to human plasma proteins (>98%), predominantly to albumin.

Metabolism:

Posaconazole primarily circulates as the parent compound in plasma. Of the circulating metabolites, the majority are glucuronide conjugates formed via UDP glucuronidation (phase 2 enzymes). Posaconazole does not have any major circulating oxidative (CYP450 mediated) metabolites. The excreted metabolites in urine and feces account for ~17% of the administered radiolabeled dose. Posaconazole is a substrate for p-glycoprotein (P-gp) efflux.

In vitro studies with human hepatic microsomes and clinical studies indicate that posaconazole is an inhibitor primarily of CYP3A4.

Excretion:

Following administration of Noxafil oral suspension, posaconazole is predominantly eliminated in the feces (71% of the radiolabeled dose up to 120 hours) with the major component eliminated as parent drug (66% of the radiolabeled dose). Renal clearance is a minor elimination pathway, with 13% of the radiolabeled dose excreted in urine up to 120 hours (<0.2% of the radiolabeled dose is parent drug).

Noxafil injection is eliminated with a mean terminal half-life (t½) of 27 hours and a total body clearance (CL) of 7.3 L/h.

Noxafil delayed-release tablet is eliminated with a mean half-life (t½) ranging between 26 to 31 hours.

Noxafil oral suspension is eliminated with a mean half-life (t½) of 35 hours (range: 20-66 hours).

Specific Populations:

No clinically significant differences in the pharmacokinetics of posaconazole were observed based on age, sex, renal impairment, and indication (prophylaxis or treatment).

Patients with Renal Impairment:

After Noxafil oral administration, there were no significant differences in the posaconazole pharmacokinetics in patients with eGFR 20 mL/minute/1.73 m^2 or higher compared to those with eGFR >80 mL/minute/1.73 m^2. Although the mean posaconazole plasma exposure (AUC) was similar in patients with eGFR less than 20 mL/minute/1.73 m^2 treated with Noxafil oral suspension to those with eGFR >80 mL/minute/1.73 m^2 treated with Noxafil oral suspension, the range of the AUC estimates was highly variable (CV=96%) in patients with eGFR less than 20 mL/minute/1.73 m^2 compared to those with eGFR >80 mL/minute/1.73 m^2 (CV<40%).Similar posaconazole pharmacokinetic results are expected after administration of Noxafil delayed-release tablets [see Use in Specific Populations (8.6)].

Patients with Hepatic Impairment:

After a single oral dose of Noxafil oral suspension 400 mg, the mean AUC was 43%, 27%, and 21% higher in subjects with mild (Child-Pugh Class A, N=6), moderate (Child-Pugh Class B, N=6), or severe (Child-Pugh Class C, N=6) hepatic impairment, respectively, compared to subjects with normal hepatic function (N=18). Compared to subjects with normal hepatic function, the mean Cmax was 1% higher, 40% higher, and 34% lower in subjects with mild, moderate, or severe hepatic impairment, respectively [see Use in Specific Populations (8.7)].

Race/Ethnicity:

In a population pharmacokinetic analysis of posaconazole, AUC was found to be 25% higher in Chinese patients relative to patients from other races/ethnicities. This higher exposure is not expected to be clinically relevant given the expected variability in posaconazole exposure [see Use in Specific Populations (8.9)].

Patients Weighing More Than 120 kg:

Weight has a clinically significant effect on posaconazole clearance. Relative to 70 kg patients, the Cavg is decreased by 25% in patients greater than 120 kg. Patients administered Noxafil weighing more than 120 kg may be at higher risk for lower posaconazole plasma concentrations compared to lower weight patients [see Use in Specific Populations (8.10)].

Pediatric Patients:

Prophylaxis of invasive Aspergillus and Candida infections in pediatric patients 2 years of age and older: A total of 12 patients 13 to 17 years of age received 600 mg/day (200 mg three times a day) of Noxafil oral suspension for prophylaxis of invasive fungal infections. Based on pharmacokinetic data in 10 of these pediatric patients, the mean steady-state Cav was similar between these patients and adults (≥18 years of age). In a study of 136 neutropenic pediatric patients 11 months to less than 18 years treated with Noxafil oral suspension, the exposure target of steady-state posaconazole Cavg between 500 ng/mL and less than 2500 ng/mL was attained in approximately 50% of patients instead of the pre-specified 90% of patients.

The mean pharmacokinetic parameters after multiple-dose administration of Noxafil injection and Noxafil PowderMix for delayed-release oral suspension in neutropenic pediatric patients 2 to less than 18 years of age (Pediatric Study 1) are shown in Table 26. Patients were enrolled into 2 age groups and received Noxafil injection and Noxafil PowderMix for delayed-release oral suspension doses at 6 mg/kg (0.6 to 1 times the recommended dose) with a maximum 300 mg dose once daily (twice daily on Day 1) [see Adverse Reactions (6.1)].

Table 26: Summary of Steady-State Geometric Mean Pharmacokinetic Parameters (% Geometric CV) After Multiple Dosing with Noxafil Injection and Noxafil PowderMix for Delayed-Release Oral Suspension 6 mg/kg [0.6 to 1 times the recommended dose] in Pediatric Patients with Neutropenia or Expected Neutropenia
Age Group | Dose Type | N | AUC0-24 hr (ng·hr/mL) | Cav [Cav = time-averaged concentrations (i.e., AUC0-24 hr/24 hr)] (ng/mL) | Cmax (ng/mL) | Cmin (ng/mL) | Tmax [Median (minimum-maximum)] (hr) | CL/F [Clearance (CL for IV and CL/F for PFS)] (L/hr)
2 to <7 years | IV | 17 | 31100 (48.9) | 1300 (48.9) | 3060 (54.1) | 626 (104.8) | 1.75 (1.57-1.83) | 3.27 (49.3)
2 to <7 years | PFS | 7 | 23000 (47.3) | 960 (47.3) | 1510 (43.4) | 542 (68.8) | 4.00 (2.17-7.92) | 4.60 (35.2)
7 to 17 years | IV | 24 | 44200 (41.5) | 1840 (41.5) | 3340 (39.4) | 1160 (60.4) | 1.77 (1.33-6.00) | 4.76 (55.7)
7 to 17 years | PFS | 12 | 25000 (184.3) | 1040 (184.3) | 1370 (178.5) | 713 (300.6) | 2.78 (0.00-4.00) | 8.39 (190.3)
IV= Noxafil injection; PFS= Noxafil PowderMix for delayed-release oral suspension; AUC0-24 = Area under the plasma concentration-time curve from time zero to 24 hr; Cmax = maximum observed concentration; Cmin = minimum observed plasma concentration; Tmax = time of maximum observed concentration; CL/F = apparent total body clearance

Based on a population pharmacokinetic model evaluating posaconazole pharmacokinetics and predicting exposures in pediatric patients, the exposure of steady-state posaconazole average concentration greater than or equal to 700 ng/mL in approximately 90% of patients is attained with the recommended dose of Noxafil injection and Noxafil PowderMix for delayed-release oral suspension.

The population pharmacokinetic analysis of posaconazole in pediatric patients from Pediatric Study 1 suggests that age, sex, renal impairment and ethnicity have no clinically meaningful effect on the pharmacokinetics of posaconazole.

Treatment of invasive aspergillosis in pediatric patients 2 years of age and older: A total of 31 patients 2 to less than 18 years of age (body weight of ≥12 kg) received pediatric dosing based on body weight of Noxafil delayed-release tablets, Noxafil Injection, and Noxafil PowderMix for delayed-release oral suspension [see Dosage and Administration (2.3].

The mean population pharmacokinetic model parameters after multiple dose administration of Noxafil delayed-release tablets, Noxafil Injection, and Noxafil PowderMix for delayed-release oral suspension in pediatric patients 2 to less than 18 years of age for the treatment of invasive aspergillosis (Pediatric Study 2) are shown in Table 27. [see Adverse Reactions (6.1)].

Table 27: Summary of Steady-State Geometric Mean Pharmacokinetic Parameters [Parameter estimates reported only for N>2 (excludes a single patient ≥2 to <12 receiving tablet and 2 patients ≥12 to <18 years receiving PFS)] (% Geometric CV) After Multiple Dosing with Noxafil Injection, Noxafil PowderMix for Delayed-Release Oral Suspension, and Noxafil Delayed-Release Tablets in Pediatric Patients being Treated for Invasive Aspergillosis
Age Group | Dose Type | N [Some patients had 2 values (1 for IV dosing and 1 for oral dosing)] | AUC0-24 hours (ng·hr/mL) | Cav [Cav = time-averaged concentrations (i.e., AUC0-24 hours/24hr)] (ng/mL) | Cmax (ng/mL) | Cmin (ng/mL) | Tmax [Median (minimum-maximum)] (hr) | CL/F [Clearance (CL for IV and CL/F for PFS or Tablet)] (L/hr)
2 to <12 years | IV | 9 | 61900 (49.8) | 2580 (49.8) | 3630 (30.8) | 1710 (82.2) | 1.50 (1.25-1.77) | 2.56 (47.8)
2 to <12 years | PFS | 6 | 45200 (30.2) | 1880 (30.2) | 2220 (26.5) | 1370 (41.8) | 7.00 (6.40-7.20) | 3.25 (34.6)
12 to <18 years | IV | 13 | 60800 (35.6) | 2530 (35.6) | 3510 (26.8) | 1740 (48.5) | 1.50 (1.30-1.63) | 4.41 (41.8)
12 to <18 years | Tablet | 10 | 47800 (52.7) | 1990 (52.7) | 2250 (48.3) | 1580 (62.6) | 7.15 (6.70-7.30) | 6.27 (52.7)
IV = Noxafil injection; PFS = Noxafil PowderMix for delayed-release oral suspension; Tablet = Noxafil delayed-release tablets; AUC0-24 hours = Area under the plasma concentration-time curve from time zero to 24 hr; Cmax = maximum observed concentration; Cmin = minimum observed plasma concentration; Tmax = time of maximum observed concentration; CL/F = apparent total body clearance

The population pharmacokinetic analysis of posaconazole in pediatric patients, including Pediatric Study 2, suggests that age, sex, ethnicity, and disease status have no clinically meaningful effect on the pharmacokinetics of posaconazole

Drug Interaction Studies:

Posaconazole is primarily metabolized via UDP glucuronidation (phase 2 enzymes) and is a substrate for p-glycoprotein (P-gp) efflux. Therefore, inhibitors or inducers of these clearance pathways may affect posaconazole plasma concentrations. A summary of drugs studied clinically with the oral suspension or another tablet formulation, which affect posaconazole concentrations, is provided in Table 28.

Table 29 and Table 30 include a summary of the drug effects of concomitant medications that may impact the absorption of posaconazole when administered as either the oral suspension or delayed-release tablets.

A clinical study in healthy volunteers also indicates that posaconazole is a strong CYP3A4 inhibitor as evidenced by a >5-fold increase in midazolam AUC. Therefore, plasma concentrations of drugs predominantly metabolized by CYP3A4 may be increased by posaconazole. A summary of the drugs studied clinically, for which plasma concentrations were affected by posaconazole, is provided in Table 31 [see Contraindications (4) and Drug Interactions (7.2) including recommendations].

Effects of Other Drugs on Noxafil and Noxafil PowderMix:

Table 28: Summary of the Effects of Coadministered Drugs on Noxafil in Healthy Volunteers
Coadministered Drug (Postulated Mechanism of Interaction) | Coadministered Drug Dose/Schedule | Noxafil Dose/Schedule | Effect on Bioavailability of Posaconazole
Coadministered Drug (Postulated Mechanism of Interaction) | Coadministered Drug Dose/Schedule | Noxafil Dose/Schedule | Change in Mean Cmax (ratio estimate [Ratio Estimate is the ratio of coadministered drug plus Noxafil to Noxafil alone for Cmax or AUC.] ; 90% CI of the ratio estimate) | Change in Mean AUC (ratio estimate; 90% CI of the ratio estimate)
Efavirenz (UDP-G Induction) | 400 mg once daily × 10 and 20 days | 400 mg (oral suspension) twice daily × 10 and 20 days | ↓45% (0.55; 0.47-0.66) | ↓ 50% (0.50; 0.43-0.60)
Fosamprenavir (unknown mechanism) | 700 mg twice daily × 10 days | 200 mg once daily on the 1st day, 200 mg twice daily on the 2nd day, then 400 mg twice daily × 8 Days | ↓21% 0.79 (0.71-0.89) | ↓23% 0.77 (0.68-0.87)
Rifabutin (UDP-G Induction) | 300 mg once daily × 17 days | 200 mg (tablets) once daily × 10 days [The tablet refers to a non-commercial tablet formulation without polymer.] | ↓ 43% (0.57; 0.43-0.75) | ↓ 49% (0.51; 0.37-0.71)
Phenytoin (UDP-G Induction) | 200 mg once daily × 10 days | 200 mg (tablets) once daily × 10 days | ↓ 41% (0.59; 0.44-0.79) | ↓ 50% (0.50; 0.36-0.71)

Noxafil Oral Suspension: Concomitant administration of Noxafil oral suspension with drugs affecting gastric pH or gastric motility results in lower posaconazole exposure. (see Table 29.)

Table 29: The Effects of Concomitant Medications that Affect the Gastric pH and Gastric Motility on the Pharmacokinetics of Noxafil Oral Suspension in Healthy Volunteers
Coadministered Drug (Postulated Mechanism of Interaction) | Coadministered Drug Dose/Schedule | Noxafil Dose/Schedule | Effect on Bioavailability of Posaconazole
Coadministered Drug (Postulated Mechanism of Interaction) | Coadministered Drug Dose/Schedule | Noxafil Dose/Schedule | Change in Mean Cmax (ratio estimate [Ratio Estimate is the ratio of coadministered drug plus Noxafil to coadministered drug alone for Cmax or AUC.] ; 90% CI of the ratio estimate) | Change in Mean AUC (ratio estimate; 90% CI of the ratio estimate)
Cimetidine (Alteration of gastric pH) | 400 mg twice daily × 10 days | 200 mg (tablets) once daily × 10 days [The tablet refers to a non-commercial tablet formulation without polymer.] | ↓ 39% (0.61; 0.53-0.70) | ↓ 39% (0.61; 0.54-0.69)
Esomeprazole (Increase in gastric pH) [The drug interactions associated with the oral suspension are also relevant for the delayed-release tablet with the exception of Esomeprazole and Metoclopramide.] | 40 mg every morning × 3 days | 400 mg (oral suspension) single dose | ↓ 46% (0.54; 0.43-0.69) | ↓ 32% (0.68; 0.57-0.81)
Metoclopramide (Increase in gastric motility) | 10 mg three times a day × 2 days | 400 mg (oral suspension) single dose | ↓ 21% (0.79; 0.72-0.87) | ↓ 19% (0.81; 0.72-0.91)

Noxafil Delayed-Release Tablets: Concomitant administration of Noxafil delayed-release tablets with drugs affecting gastric pH or gastric motility did not demonstrate any significant effects on posaconazole pharmacokinetic exposure (see Table 30).

Table 30: The Effects of Concomitant Medications that Affect the Gastric pH and Gastric Motility on the Pharmacokinetics of Noxafil Delayed-Release Tablets in Healthy Volunteers
Coadministered Drug | Administration Arms | Change in Cmax (ratio estimate [Ratio Estimate is the ratio of coadministered drug plus Noxafil to Noxafil alone for Cmax or AUC0-last.] ; 90% CI of the ratio estimate) | Change in AUC0-last (ratio estimate; 90% CI of the ratio estimate)
Mylanta® Ultimate strength liquid (Increase in gastric pH) | 25.4 mEq/5 mL, 20 mL | ↑6% (1.06; 0.90 -1.26)↑ | ↑4% (1.04; 0.90 -1.20)
Ranitidine (Zantac®) (Alteration in gastric pH) | 150 mg (morning dose of 150 mg Ranitidine twice daily) | ↑4% (1.04; 0.88 -1.23)↑ | ↓3% (0.97; 0.84 -1.12)
Esomeprazole (Nexium®) (Increase in gastric pH) | 40 mg (every morning for 5 days, Day -4 to 1) | ↑2% (1.02; 0.88-1.17)↑ | ↑5% (1.05; 0.89 -1.24)
Metoclopramide (Reglan®) (Increase in gastric motility) | 15 mg four times daily for 2 days (Day -1 and 1) | ↓14% (0.86, 0.73,1.02) | ↓7% (0.93, 0.803,1.07)

Noxafil PowderMix for Delayed-Release Oral Suspension: Concomitant administration of Noxafil PowderMix for delayed-release oral suspension with drugs affecting gastric pH or gastric motility would not be expected to demonstrate any significant effects on posaconazole pharmacokinetic exposure based on similarity to the delayed-release tablets.

An in vitro dissolution study was conducted to evaluate the impact of alcohol (5, 10, 20, and 40%) on the dissolution of Noxafil PowderMix delayed-release oral suspension. The study showed alcohol-induced dose-dumping potential with the Noxafil PowderMix delayed-release oral suspension [see Drug Interactions (7.1)].

Effects of Noxafil and Noxafil PowderMix on Other Drugs:

Table 31: Summary of the Effects of Noxafil on Coadministered Drugs in Healthy Adult Volunteers and Patients
Coadministered Drug (Postulated Mechanism of Interaction is Inhibition of CYP3A4 by posaconazole) | Coadministered Drug Dose/Schedule | Noxafil Dose/ Schedule | Effect on Bioavailability of Coadministered Drugs
Coadministered Drug (Postulated Mechanism of Interaction is Inhibition of CYP3A4 by posaconazole) | Coadministered Drug Dose/Schedule | Noxafil Dose/ Schedule | Change in Mean Cmax (ratio estimate [Ratio Estimate is the ratio of coadministered drug plus Noxafil to coadministered drug alone for Cmax or AUC.] ; 90% CI of the ratio estimate) | Change in Mean AUC (ratio estimate; 90% CI of the ratio estimate)
Sirolimus | 2-mg single oral dose | 400 mg (oral suspension) twice daily x 16 days | ↑ 572% (6.72; 5.62-8.03) | ↑ 788% (8.88; 7.26-10.9)
Cyclosporine | Stable maintenance dose in heart transplant recipients | 200 mg (tablets) once daily x 10 days [The tablet refers to a non-commercial tablet formulation without polymer.] | ↑ Cyclosporine whole blood trough concentrations Cyclosporine dose reductions of up to 29% were required
Tacrolimus | 0.05-mg/kg single oral dose | 400 mg (oral suspension) twice daily x 7 days | ↑ 121% (2.21; 2.01-2.42) | ↑ 358% (4.58; 4.03-5.19)
Simvastatin | 40-mg single oral dose | 100 mg (oral suspension) once daily x 13 days | Simvastatin ↑ 841% (9.41, 7.13-12.44) Simvastatin Acid ↑ 817% (9.17, 7.36-11.43) | Simvastatin ↑ 931% (10.31, 8.40-12.67) Simvastatin Acid ↑634% (7.34, 5.82-9.25)
 |  | 200 mg (oral suspension) once daily x 13 days | Simvastatin ↑ 1041% (11.41, 7.99-16.29) Simvastatin Acid ↑851% (9.51, 8.15-11.10) | Simvastatin ↑ 960% (10.60, 8.63-13.02) Simvastatin Acid ↑ 748% (8.48, 7.04-10.23)
Midazolam | 0.4-mg single intravenous dose [The mean terminal half-life of midazolam was increased from 3 hours to 7 to 11 hours during coadministration with Noxafil.] | 200 mg (oral suspension) twice daily x 7 days | ↑ 30% (1.3; 1.13-1.48) | ↑ 362% (4.62; 4.02-5.3)
 | 0.4-mg single intravenous dose | 400 mg (oral suspension) twice daily x 7 days | ↑62% (1.62; 1.41-1.86) | ↑524% (6.24; 5.43-7.16)
 | 2-mg single oral dose | 200 mg (oral suspension) once daily x 7 days | ↑ 169% (2.69; 2.46-2.93) | ↑ 470% (5.70; 4.82-6.74)
 | 2-mg single oral dose | 400 mg (oral suspension) twice daily x 7 days | ↑ 138% (2.38; 2.13-2.66) | ↑ 397% (4.97; 4.46-5.54)
Rifabutin | 300 mg once daily x 17 days | 200 mg (tablets) once daily x 10 days | ↑ 31% (1.31; 1.10-1.57) | ↑ 72% (1.72;1.51-1.95)
Phenytoin | 200 mg once daily PO x 10 days | 200 mg (tablets) once daily x 10 days | ↑ 16% (1.16; 0.85-1.57) | ↑ 16% (1.16; 0.84-1.59)
Ritonavir | 100 mg once daily x 14 days | 400 mg (oral suspension) twice daily x 7 days | ↑ 49% (1.49; 1.04-2.15) | ↑ 80% (1.8;1.39-2.31)
Atazanavir | 300 mg once daily x 14 days | 400 mg (oral suspension) twice daily x 7 days | ↑ 155% (2.55; 1.89-3.45) | ↑ 268% (3.68; 2.89-4.70)
Atazanavir/ritonavir boosted regimen | 300 mg/100 mg once daily x 14 days | 400 mg (oral suspension) twice daily x 7 days | ↑ 53% (1.53; 1.13-2.07) | ↑ 146% (2.46; 1.93-3.13)

12.4 Microbiology

Mechanism of Action

Posaconazole blocks the synthesis of ergosterol, a key component of the fungal cell membrane, through the inhibition of cytochrome P-450 dependent enzyme lanosterol 14α-demethylase responsible for the conversion of lanosterol to ergosterol in the fungal cell membrane. This results in an accumulation of methylated sterol precursors and a depletion of ergosterol within the cell membrane thus weakening the structure and function of the fungal cell membrane. This may be responsible for the antifungal activity of posaconazole.

Resistance

Clinical isolates of Candida albicans and Candida glabrata with decreased susceptibility to posaconazole were observed in oral swish samples taken during prophylaxis with posaconazole and fluconazole, suggesting a potential for development of resistance. These isolates also showed reduced susceptibility to other azoles, suggesting cross-resistance between azoles. The clinical significance of this finding is not known.

Antimicrobial Activity

Posaconazole has been shown to be active against most isolates of the following microorganisms, both in vitro and in clinical infections [see Indications and Usage (1)].

Microorganisms

Aspergillus spp. and Candida spp.

Susceptibility Testing

For specific information regarding susceptibility test interpretive criteria and associated test methods and quality control standards recognized by FDA for this drug, please see: https://www.fda.gov/STIC .

13 NONCLINICAL TOXICOLOGY

13.1 Carcinogenesis, Mutagenesis, Impairment of Fertility

Carcinogenesis

No drug-related neoplasms were recorded in rats or mice treated with posaconazole for 2 years at doses higher than the clinical dose. In a 2 year carcinogenicity study, rats were given posaconazole orally at doses up to 20 mg/kg (females), or 30 mg/kg (males). These doses are equivalent to 3.9- or 3.5 times the exposure achieved with a 400 mg twice daily oral suspension regimen, respectively, based on steady-state AUC in healthy volunteers administered a high-fat meal (400 mg twice daily oral suspension regimen). In the mouse study, mice were treated at oral doses up to 60 mg/kg/day or 4.8 times the exposure achieved with a 400 mg twice daily oral suspension regimen.

Mutagenesis

Posaconazole was not genotoxic or clastogenic when evaluated in bacterial mutagenicity (Ames), a chromosome aberration study in human peripheral blood lymphocytes, a Chinese hamster ovary cell mutagenicity study, and a mouse bone marrow micronucleus study.

Impairment of Fertility

Posaconazole had no effect on fertility of male rats at a dose up to 180 mg/kg (1.7 x the 400 mg twice daily oral suspension regimen based on steady-state plasma concentrations in healthy volunteers) or female rats at a dose up to 45 mg/kg (2.2 x the 400 mg twice daily oral suspension regimen).

14 CLINICAL STUDIES

14.1 Treatment of Invasive Aspergillosis with Noxafil Injection and Noxafil Delayed-Release Tablets

Aspergillosis Treatment Study (NCT01782131) was a randomized, double-blind, controlled trial which evaluated the safety and efficacy of Noxafil injection and Noxafil delayed-release tablets versus voriconazole for primary treatment of invasive fungal disease caused by Aspergillus species. Eligible patients had proven, probable, or possible invasive fungal infections per the European Organization for Research and Treatment of Cancer/Mycoses Study Group, EORTC/MSG criteria. Patients were stratified by risk for mortality or poor outcome where high risk included a history of allogeneic bone marrow transplant, liver transplant, or relapsed leukemia undergoing salvage chemotherapy. The median age of patients was 57 years (range: 14-91 years), with 27.8% of patients aged ≥65 years; 5 patients were pediatric patients 14-16 years of age, of whom 3 were treated with Noxafil and 2 with voriconazole. The majority of patients were male (59.8%) and white (67.1%). With regard to risk factors for invasive aspergillosis, approximately two-thirds of the patients in the study had a recent history of neutropenia, while approximately 20% with a history of an allogeneic stem cell transplant. Over 80% of subjects in each treatment group had infection limited to the lower respiratory tract (primarily lung), while approximately 11% to 13% also had infection in another organ. Invasive aspergillosis was proven or probable in 58.1% of patients as classified by independent adjudicators blinded to study treatment assignment. At least one Aspergillus species was identified in 21% of the patients; A. fumigatus and A. flavus were the most common pathogens identified.

Patients randomized to receive Noxafil were given a dose of 300 mg once daily (twice daily on Day 1) IV or tablet. Patients randomized to receive voriconazole were given a dose of 6 mg/kg twice daily Day 1 followed by 4 mg/kg twice daily IV, or oral 300 mg twice daily Day 1 followed by 200 mg twice daily. The recommended initial route of administration was IV; however, patients could begin oral therapy if clinically stable and able to tolerate oral dosing. The transition from IV to oral therapy occurred when the patient was clinically stable. The protocol recommended duration of therapy was 84 days with a maximum allowed duration of 98 days. Median treatment duration was 67 days for Noxafil patients and 64 days for voriconazole patients. Overall, 55% to 60% of patients began treatment with the IV formulation with a median duration of 9 days for the initial IV dosing.

The Intent to Treat (ITT) population included all patients randomized and receiving at least one dose of study treatment. All-cause mortality through Day 42 in the overall population (ITT) was 15.3% for Noxafil patients compared to 20.6% for voriconazole patients for an adjusted treatment difference of -5.3% with a 95% confidence interval of -11.6 to 1.0%. Consistent results were seen in patients with proven or probable invasive aspergillosis per EORTC criteria (see Table 32).

Table 32: Noxafil Injection and Noxafil Delayed-Release Tablets Invasive Aspergillosis Treatment Study: All-Cause Mortality Through Day 42
 | Noxafil Injection and Delayed-Release Tablets |  | Voriconazole
Population | N | n (%) | N | n (%) | Difference [Adjusted treatment difference based on Miettinen and Nurminen’s method stratified by randomization factor (risk for mortality/poor outcome), using Cochran-Mantel-Haenszel weighting scheme.] (95% CI)
Intent to Treat | 288 | 44 (15.3) | 287 | 59 (20.6) | -5.3 (-11.6, 1.0)
Proven/Probable Invasive Aspergillosis | 163 | 31 (19.0) | 171 | 32 (18.7) | 0.3 (-8.2, 8.8)

Global clinical response at Week 6 was assessed by a blinded, independent adjudication committee based upon prespecified clinical, radiologic, and mycologic criteria. In the subgroup of patients with proven or probable invasive aspergillosis per EORTC criteria, the global clinical response of success (complete or partial response) at Week 6 was seen in 44.8% for Noxafil-treated patients compared to 45.6% for voriconazole-treated patients (see Table 33).

Table 33: Noxafil Injection and Noxafil Delayed-Release Tablets Invasive Aspergillosis Treatment Study: Successful Global Clinical Response [Successful Global Clinical Response was defined as survival with a partial or complete response.] at Week 6
 | Posaconazole |  | Voriconazole
Population | N | Success | N | Success | Difference [Adjusted treatment difference based on Miettinen and Nurminen’s method stratified by randomization factor (risk for mortality/poor outcome), using Cochran-Mantel-Haenszel weighting scheme.] (95% CI)
Proven/Probable Invasive Aspergillosis | 163 | 73 (44.8) | 171 | 78 (45.6) | -0.6 (-11.2, 10.1)

14.2 Prophylaxis of Aspergillus and Candida Infections with Noxafil Oral Suspension

Two randomized, controlled studies were conducted using Noxafil as prophylaxis for the prevention of invasive fungal infections (IFIs) among patients at high risk due to severely compromised immune systems.

The first study (Noxafil Oral Suspension Study 1) was a randomized, double-blind trial that compared Noxafil oral suspension (200 mg three times a day) with fluconazole capsules (400 mg once daily) as prophylaxis against invasive fungal infections in allogeneic hematopoietic stem cell transplant (HSCT) recipients with Graft versus Host Disease (GVHD). Efficacy of prophylaxis was evaluated using a composite endpoint of proven/probable IFIs, death, or treatment with systemic antifungal therapy (patients may have met more than one of these criteria). This assessed all patients while on study therapy plus 7 days and at 16 weeks post-randomization. The mean duration of therapy was comparable between the 2 treatment groups (80 days, Noxafil oral suspension; 77 days, fluconazole). Table 34 contains the results from Noxafil Oral Suspension Study 1.

Table 34: Results from Blinded Clinical Study in Prophylaxis of IFI in All Randomized Patients with Hematopoietic Stem Cell Transplant (HSCT) and Graft-vs.-Host Disease (GVHD): Noxafil Oral Suspension Study 1
 | Posaconazole n=301 | Fluconazole n=299
On therapy plus 7 days
Clinical Failure [Patients may have met more than one criterion defining failure.] | 50 (17%) | 55 (18%)
Failure due to:
Proven/Probable IFI | 7 (2%) | 22 (7%)
(Aspergillus) | 3 (1%) | 17 (6%)
(Candida) | 1 (<1%) | 3 (1%)
(Other) | 3 (1%) | 2 (1%)
All Deaths | 22 (7%) | 24 (8%)
Proven/probable fungal infection prior to death | 2 (<1%) | 6 (2%)
SAF [Use of systemic antifungal therapy (SAF) criterion is based on protocol definitions (empiric/IFI usage >4 consecutive days).] | 27 (9%) | 25 (8%)
Through 16 weeks
Clinical Failure, [95% confidence interval (posaconazole-fluconazole) = (-11.5%, + 3.7%).] | 99 (33%) | 110 (37%)
Failure due to:
Proven/Probable IFI | 16 (5%) | 27 (9%)
(Aspergillus) | 7 (2%) | 21 (7%)
(Candida) | 4 (1%) | 4 (1%)
(Other) | 5 (2%) | 2 (1%)
All Deaths | 58 (19%) | 59 (20%)
Proven/probable fungal infection prior to death | 10 (3%) | 16 (5%)
SAF | 26 (9%) | 30 (10%)
Event free lost to follow-up [Patients who are lost to follow-up (not observed for 112 days), and who did not meet another clinical failure endpoint. These patients were considered failures.] | 24 (8%) | 30 (10%)

The second study (Noxafil Oral Suspension Study 2) was a randomized, open-label study that compared Noxafil oral suspension (200 mg 3 times a day) with fluconazole suspension (400 mg once daily) or itraconazole oral solution (200 mg twice a day) as prophylaxis against IFIs in neutropenic patients who were receiving cytotoxic chemotherapy for AML or MDS. As in Noxafil Oral Suspension Study 1, efficacy of prophylaxis was evaluated using a composite endpoint of proven/probable IFIs, death, or treatment with systemic antifungal therapy (Patients might have met more than one of these criteria). This study assessed patients while on treatment plus 7 days and 100 days post-randomization. The mean duration of therapy was comparable between the 2 treatment groups (29 days, posaconazole; 25 days, fluconazole or itraconazole). Table 35 contains the results from Noxafil Oral Suspension Study 2.

Table 35: Results from Open-Label Clinical Study 2 in Prophylaxis of IFI in All Randomized Patients with Hematologic Malignancy and Prolonged Neutropenia: Noxafil Oral Suspension Study 2
 | Posaconazole n=304 | Fluconazole/Itraconazole n=298
On therapy plus 7 days
Clinical Failure [95% confidence interval (posaconazole-fluconazole/itraconazole) = (-22.9%, -7.8%).] , [Patients may have met more than one criterion defining failure.] | 82 (27%) | 126 (42%)
Failure due to:
Proven/Probable IFI | 7 (2%) | 25 (8%)
(Aspergillus) | 2 (1%) | 20 (7%)
(Candida) | 3 (1%) | 2 (1%)
(Other) | 2 (1%) | 3 (1%)
All Deaths | 17 (6%) | 25 (8%)
Proven/probable fungal infection prior to death | 1 (<1%) | 2 (1%)
SAF [Use of systemic antifungal therapy (SAF) criterion is based on protocol definitions (empiric/IFI usage >3 consecutive days).] | 67 (22%) | 98 (33%)
Through 100 days post-randomization
Clinical Failure | 158 (52%) | 191 (64%)
Failure due to:
Proven/Probable IFI | 14 (5%) | 33 (11%)
(Aspergillus) | 2 (1%) | 26 (9%)
(Candida) | 10 (3%) | 4 (1%)
(Other) | 2 (1%) | 3 (1%)
All Deaths | 44 (14%) | 64 (21%)
Proven/probable fungal infection prior to death | 2 (1%) | 16 (5%)
SAF | 98 (32%) | 125 (42%)
Event free lost to follow-up [Patients who are lost to follow-up (not observed for 100 days), and who did not meet another clinical failure endpoint. These patients were considered failures.] | 34 (11%) | 24 (8%)

In summary, 2 clinical studies of prophylaxis were conducted with the Noxafil oral suspension. As seen in the accompanying tables (Table 34 and Table 35), clinical failure represented a composite endpoint of breakthrough IFI, mortality and use of systemic antifungal therapy. In Noxafil Oral Suspension Study 1 (Table 34), the clinical failure rate of posaconazole (33%) was similar to fluconazole (37%), (95% CI for the difference posaconazole–comparator -11.5% to 3.7%) while in Noxafil Oral Suspension Study 2 (Table 35) clinical failure was lower for patients treated with posaconazole (27%) when compared to patients treated with fluconazole or itraconazole (42%), (95% CI for the difference posaconazole–comparator -22.9% to -7.8%).

All-cause mortality was similar at 16 weeks for both treatment arms in Noxafil Oral Suspension Study 1 [POS 58/301 (19%) vs. FLU 59/299 (20%)]; all-cause mortality was lower at 100 days for Noxafil-treated patients in Noxafil Oral Suspension Study 2 [POS 44/304 (14%) vs. FLU/ITZ 64/298 (21%)]. Both studies demonstrated fewer breakthrough infections caused by Aspergillus species in patients receiving Noxafil prophylaxis when compared to patients receiving fluconazole or itraconazole.

14.3 Treatment of Oropharyngeal Candidiasis with Noxafil Oral Suspension

Noxafil Oral Suspension Study 3 was a randomized, controlled, evaluator-blinded study in HIV-infected patients with oropharyngeal candidiasis. Patients were treated with Noxafil or fluconazole oral suspension (both Noxafil and fluconazole were given as follows: 100 mg twice a day for 1 day followed by 100 mg once a day for 13 days).

Clinical and mycological outcomes were assessed after 14 days of treatment and at 4 weeks after the end of treatment. Patients who received at least 1 dose of study medication and had a positive oral swish culture of Candida species at baseline were included in the analyses (see Table 36). The majority of the subjects had C. albicans as the baseline pathogen.

Clinical success at Day 14 (complete or partial resolution of all ulcers and/or plaques and symptoms) and clinical relapse rates (recurrence of signs or symptoms after initial cure or improvement) 4 weeks after the end of treatment were similar between the treatment arms (see Table 36).

Mycologic eradication rates (absence of colony forming units in quantitative culture at the end of therapy, Day 14), as well as mycologic relapse rates (4 weeks after the end of treatment) were also similar between the treatment arms (see Table 36).

Table 36: Noxafil Oral Suspension Clinical Success, Mycological Eradication, and Relapse Rates in Oropharyngeal Candidiasis
 | Noxafil | Fluconazole
Clinical Success at End of Therapy (Day 14) | 155/169 (91.7%) | 148/160 (92.5%)
Clinical Relapse (4 Weeks after End of Therapy) | 45/155 (29.0%) | 52/148 (35.1%)
Mycological Eradication (absence of CFU) at End of Therapy (Day 14) | 88/169 (52.1%) | 80/160 (50.0%)
Mycological Relapse (4 Weeks after End of Treatment) | 49/88 (55.6%) | 51/80 (63.7%)

Mycologic response rates, using a criterion for success as a posttreatment quantitative culture with ≤20 colony forming units (CFU/mL) were also similar between the two groups (Noxafil 68.0%, fluconazole 68.1%). The clinical significance of this finding is unknown.

14.4 Noxafil Oral Suspension Treatment of Oropharyngeal Candidiasis Refractory to Treatment with Fluconazole or Itraconazole

Noxafil Oral Suspension Study 4 was a noncomparative study of Noxafil oral suspension in HIV-infected subjects with OPC that was refractory to treatment with fluconazole or itraconazole. An episode of OPC was considered refractory if there was failure to improve or worsening of OPC after a standard course of therapy with fluconazole greater than or equal to 100 mg/day for at least 10 consecutive days or itraconazole 200 mg/day for at least 10 consecutive days and treatment with either fluconazole or itraconazole had not been discontinued for more than 14 days prior to treatment with Noxafil. Of the 199 subjects enrolled in this study, 89 subjects met these strict criteria for refractory infection.

Forty-five subjects with refractory OPC were treated with Noxafil oral suspension 400 mg twice daily for 3 days, followed by 400 mg once daily for 25 days with an option for further treatment during a 3 month maintenance period. Following a dosing amendment, a further 44 subjects were treated with posaconazole 400 mg twice daily for 28 days. The efficacy of Noxafil was assessed by the clinical success (cure or improvement) rate after 4 weeks of treatment. The clinical success rate was 74.2% (66/89). The clinical success rates for both the original and the amended dosing regimens were similar (73.3% and 75.0%, respectively).

16 HOW SUPPLIED/STORAGE AND HANDLING

16.1 How Supplied

Noxafil Injection

Noxafil injection is a clear, colorless to yellow sterile liquid in single-dose Type I glass vials closed with bromobutyl rubber stopper and aluminum seal containing 300 mg of posaconazole in 16.7 mL of solution (18 mg of posaconazole per mL) (NDC 0085-4331-01).

Noxafil Delayed-Release Tablets

Noxafil delayed-release tablets are yellow, coated, oblong, debossed with "100" on one side containing 100 mg of posaconazole. Bottles with child-resistant closures of 60 delayed-release tablets (NDC 0085-4324-02).

Noxafil Oral Suspension

Noxafil oral suspension is a white, cherry-flavored oral suspension in 4-ounce (123 mL) amber glass bottles with child-resistant closures containing 105 mL of suspension (40 mg of posaconazole per mL).Supplied with each oral suspension bottle is a plastic dosing spoon calibrated for measuring 2.5 mL and 5 mL doses (NDC 0085-1328-01).

Noxafil PowderMix for Delayed-Release Oral Suspension

Noxafil PowderMix for delayed-release oral suspension is supplied as:

- Package A: a kit with 8 child-resistant single-use packets of Noxafil PowderMix for delayed-release oral suspension 300 mg, two 3 mL (green) notched tip syringes, two 10 mL (blue) notched tip syringes, two mixing cups, one mixing liquid bottle, one bottle adapter for the mixing liquid bottle and Instructions for Use.
- Package B: a box of six 3 mL (green) and six 10 mL (blue) notched tip syringes for additional supply.
- Packages A and B are supplied separately.

NDC 0085-2224-02 unit of use carton with 8 packets.

NDC 0085-2224-01 individual packet.

16.2 Storage and Handling

Noxafil Injection

Store Noxafil injection vial refrigerated at 2 to 8°C (36 to 46°F). Storage conditions for the diluted Noxafil infusion solution are presented in another section of the prescribing information [see Dosage and Administration (2.5)].

Noxafil Delayed-Release Tablets

Store at 20 to 25°C (68 to 77°F), excursions permitted to 15 to 30°C (59 to 86°F) [see USP Controlled Room Temperature].

Noxafil Oral Suspension

Store at 25°C (77°F); excursions permitted to 15 to 30°C (59 to 86°F) [see USP Controlled Room Temperature]. DO NOT FREEZE.

Noxafil PowderMix for Delayed-Release Oral Suspension

Store the entire kit at 20 to 25°C (68 to 77°F), excursions permitted to 15 to 30°C (59 to 86°F) in a clean, dry place. Do not open foil packet containing Noxafil PowderMix for delayed-release oral suspension until ready for use. Storage conditions for the reconstituted solution are presented in another section of the prescribing information [see Dosage and Administration (2.10)].

17 PATIENT COUNSELING INFORMATION

Advise the patient to read the FDA-approved patient labeling (Patient Information and Instructions for Use).

Important Administration Instructions

Noxafil Delayed-Release Tablets

Advise patients that Noxafil delayed-release tablets must be swallowed whole and not divided, crushed, or chewed.

Instruct patients that if they miss a dose, they should take it as soon as they remember. If they do not remember until it is within 12 hours of the next dose, they should be instructed to skip the missed dose and go back to the regular schedule. Patients should not double their next dose or take more than the prescribed dose.

Noxafil Oral Suspension

Advise patients to take each dose of Noxafil oral suspension during or immediately (i.e., within 20 minutes) following a full meal. In patients who cannot eat a full meal, each dose of Noxafil oral suspension should be administered with a liquid nutritional supplement or an acidic carbonated beverage (e.g., ginger ale) in order to enhance absorption.

Instruct patients that if they miss a dose, they should take it as soon as they remember. However, if it is almost time for the next dose, they should be instructed to skip the missed dose and go back to the regular schedule. Patients should not double their next dose or take more than the prescribed dose.

Noxafil PowderMix for Delayed-Release Oral Suspension

Instruct parents and/or caregivers that ONLY the provided notched tip syringes can be used to administer Noxafil PowderMix for delayed-release oral suspension to pediatric patients.

Advise patients to take Noxafil PowderMix for delayed-release oral suspension with food.

Drug Interactions

Advise patients to inform their physician immediately if they:

- develop severe diarrhea or vomiting.
- are currently taking drugs that are known to prolong the QTc interval and are metabolized through CYP3A4.
- are currently taking a cyclosporine or tacrolimus, or they notice swelling in an arm or leg or shortness of breath.
- are taking other drugs or before they begin taking other drugs as certain drugs can decrease or increase the plasma concentrations of posaconazole.

Serious and Potentially Serious Adverse Reactions

Advise patients to inform their physician immediately if they:

- notice a change in heart rate or heart rhythm or have a heart condition or circulatory disease. Noxafil can be administered with caution to patients with potentially proarrhythmic conditions.
- are pregnant, plan to become pregnant, or are nursing.
- have liver disease or develop itching, nausea or vomiting, their eyes or skin turn yellow, they feel more tired than usual or feel like they have the flu.
- have ever had an allergic reaction to other antifungal medicines such as ketoconazole, fluconazole, itraconazole, or voriconazole.

Hereditary Fructose Intolerance (HFI)

Inform patients and caregivers that Noxafil PowderMix for delayed-release oral suspension contains sorbitol and can be life-threatening when administered to patients with hereditary fructose intolerance (HFI) [see Warnings and Precautions (5.9)]. Inquire for symptoms of sorbitol/fructose and/or sucrose intolerance before administration.

Manuf. for: Merck Sharp & Dohme LLC
Rahway, NJ 07065, USA

For patent information: www.msd.com/research/patent

The trademarks referenced herein are owned by their respective companies.

Copyright © 2006-2026 Merck & Co., Inc., Rahway, NJ, USA, and its affiliates.
All rights reserved.

uspi-mk5592-mf-2601r050

Patient Information
NOXAFIL® (NOX-a-fil)
(posaconazole) injection
NOXAFIL® (NOX-a-fil)
(posaconazole) delayed-release tablets
NOXAFIL® (NOX-a-fil)
(posaconazole) oral suspension
NOXAFIL® (NOX-a-fil) POWDERMIX
(posaconazole) for delayed-release oral suspension

What is Noxafil and Noxafil PowderMix?
Noxafil (which refers to injection, delayed-release tablets, and oral suspension) and Noxafil PowderMix (for delayed-release oral suspension) are prescription medicines used in adults and children to help prevent or treat fungal infections that can spread throughout your body (invasive fungal infections). These infections are caused by fungi called Aspergillus or Candida. Noxafil and Noxafil PowderMix are used in people who have an increased chance of getting these infections due to a weak immune system. These include people who have had a hematopoietic stem cell transplantation (bone marrow transplant) with graft versus host disease or those with a low white blood cell count due to chemotherapy for blood cancers (hematologic malignancies).

Noxafil injection is used for:

- prevention of fungal infections in adults and children 2 years of age and older who weigh 22 lbs (10 kg) or greater.
- treatment of fungal infections in adults and children 2 years of age and older who weigh 22 lbs (10 kg) or greater.

Noxafil delayed-release tablets are used for:

- prevention of fungal infections in adults and children 2 years of age and older who weigh greater than 88 lbs (40 kg).
- treatment of fungal infections in adults and children 2 years of age and older who weigh greater than 88 lbs (40 kg).

Noxafil oral suspension is used for:

- prevention of fungal infections in adults and children 13 years of age and older.

Noxafil PowderMix for delayed-release oral suspension is used for:

- prevention of fungal infections in children 2 years of age and older who weigh 22 lbs to 88 lbs (10 kg to 40 kg).
- treatment of fungal infections in children 2 years of age and older who weigh 22 lbs to 88 lbs (10 kg to 40 kg).

Noxafil oral suspension is also used to treat a fungal infection called “thrush” caused by Candida in your mouth or throat area. Noxafil oral suspension can be used as the first treatment for thrush, or as another treatment for thrush after itraconazole or fluconazole treatment has not worked.

Noxafil oral suspension is for adults and children 13 years of age and older.

It is not known if Noxafil oral suspension is safe and effective in children under 13 years of age for the treatment of thrush as the first treatment for thrush, or as another treatment for thrush after itraconazole or fluconazole treatment has not worked.

It is not known if Noxafil or Noxafil PowderMix is safe and effective in children under 2 years of age.

Do not take Noxafil or Noxafil PowderMix if you:

- are allergic to posaconazole, any of the ingredients in Noxafil or Noxafil PowderMix, or other azole antifungal medicines. See the end of this Patient Information leaflet for a complete list of ingredients in Noxafil and Noxafil PowderMix.
- are taking any of the following medicines:
  - sirolimus
  - pimozide
  - quinidine
  - certain statin medicines that lower cholesterol (atorvastatin, lovastatin, simvastatin)
  - ergot alkaloids (ergotamine, dihydroergotamine)
- have chronic lymphocytic leukemia (CLL) or small lymphocytic lymphoma (SLL) and you have just started taking venetoclax or your venetoclax dose is being slowly increased.
- are taking Noxafil PowderMix for delayed-release oral suspension and have hereditary fructose intolerance.

Ask your healthcare provider or pharmacist if you are not sure if you are taking any of these medicines.
Do not start taking a new medicine without talking to your healthcare provider or pharmacist.

Before you take Noxafil or Noxafil PowderMix, tell your healthcare provider about all of your medical conditions, including if you:

- are taking certain medicines that lower your immune system like cyclosporine or tacrolimus.
- are taking certain drugs for HIV infection, such as ritonavir, atazanavir, efavirenz, or fosamprenavir. Efavirenz and fosamprenavir can cause a decrease in the Noxafil levels in your body. Efavirenz and fosamprenavir should not be taken with Noxafil or Noxafil PowderMix.
- are taking midazolam, a hypnotic and sedative medicine.
- are taking vincristine, vinblastine and other “vinca alkaloids” (medicines used to treat cancer).
- are taking venetoclax, a medicine used to treat cancer.
- have or had liver problems.
- have or had kidney problems.
- have or had an abnormal heart rate or rhythm, heart problems, or blood circulation problems.
- are pregnant or plan to become pregnant. It is not known if Noxafil will harm your unborn baby.
- are breastfeeding or plan to breastfeed. It is not known if Noxafil passes into your breast milk. You and your healthcare provider should decide if you will take Noxafil or breastfeed. You should not do both.

Tell your healthcare provider about all the medicines you take, including prescription and over-the-counter medicines, vitamins, and herbal supplements. Noxafil and Noxafil PowderMix can affect the way other medicines work, and other medicines can affect the way Noxafil and Noxafil PowderMix work, and can cause serious side effects.
Especially tell your healthcare provider if you take:

- rifabutin or phenytoin. If you are taking these medicines, you should not take Noxafil delayed-release tablets, Noxafil oral suspension, or Noxafil PowderMix for delayed-release oral suspension.
- cimetidine or esomeprazole. If you are taking these medicines, you should not take Noxafil oral suspension.

Ask your healthcare provider or pharmacist for a list of these medicines if you are not sure.
Know the medicines you take. Keep a list of them with you to show your healthcare provider or pharmacist when you get a new medicine.

How should I take Noxafil or Noxafil PowderMix?

- Do not switch between Noxafil oral suspension and Noxafil delayed-release tablets or Noxafil PowderMix for delayed-release oral suspension.
- Take Noxafil or Noxafil PowderMix exactly as your healthcare provider tells you to take it.
- Your healthcare provider will tell you how much Noxafil or Noxafil PowderMix to take and when to take it.
- Take Noxafil or Noxafil PowderMix for as long as your healthcare provider tells you to take it.
- If you take too much Noxafil or Noxafil PowderMix, call your healthcare provider or go to the nearest hospital emergency room right away.
- Noxafil injection is usually given over 30 to 90 minutes through a plastic tube placed in your vein.
- Noxafil delayed-release tablets:
  - Take Noxafil delayed-release tablets with or without food.
  - Take Noxafil delayed-release tablets whole. Do not break, crush, or chew Noxafil delayed-release tablets before swallowing. If you cannot swallow Noxafil delayed-release tablets whole, tell your healthcare provider. You may need a different medicine.
  - If you miss a dose, take it as soon as you remember and then take your next scheduled dose at its regular time. If it is within 12 hours of your next dose, do not take the missed dose. Skip the missed dose and go back to your regular schedule. Do not double your next dose or take more than your prescribed dose.
- Noxafil oral suspension:
  - Shake Noxafil oral suspension well before use.
  - Take each dose of Noxafil oral suspension during or within 20 minutes after a full meal. If you cannot eat a full meal, take each dose of Noxafil oral suspension with a liquid nutritional supplement or an acidic carbonated beverage, like ginger ale.
  - A measured dosing spoon comes with your Noxafil oral suspension and is marked for doses of 2.5 mL and 5 mL. See Figure A.
    Figure A
  - Rinse the spoon with water after each dose of Noxafil oral suspension and before you store it away.
  - If you miss a dose, take it as soon as you remember. However, if it is almost time for the next dose, skip the missed dose and go back to the regular dosing schedule. Do not take a double dose to make up for the missed dose or take more than your prescribed dose.
- Noxafil PowderMix for delayed-release oral suspension:
  - Before giving the first dose of Noxafil PowderMix for delayed-release oral suspension, read the Instructions for Use booklet that comes with Noxafil PowderMix for delayed-release oral suspension for information about the correct way to mix and give a dose of Noxafil PowderMix for delayed-release oral suspension to your child. Keep the booklet and follow it each time you prepare the medicine. Bring this booklet to your child’s appointments.
  - If you have questions about how to mix or give Noxafil PowderMix, talk with your healthcare provider or pharmacist.
  - Only use the mixing liquid that comes with the kit to prepare Noxafil PowderMix.
  - After mixing, measure the prescribed dose with notched tip syringe provided with the kit. Only use the notched tip syringes that come with the kit to prepare and give the medicine.
  - Give the dose within 1 hour of mixing the suspension. Give with food.
  - If your child does not take all of the prescribed dose or spits some of it out, call your healthcare provider to find out what to do.

Follow the instructions from your healthcare provider on how much Noxafil or Noxafil PowderMix you should take and when to take it.

What are the possible side effects of Noxafil or Noxafil PowderMix?

Noxafil or Noxafil PowderMix may cause serious side effects, including:

- drug interactions with cyclosporine or tacrolimus. If you take Noxafil or Noxafil PowderMix with cyclosporine or tacrolimus, your blood levels of cyclosporine or tacrolimus may increase. Serious side effects can happen in your kidney or brain if you have high levels of cyclosporine or tacrolimus in your blood. Your healthcare provider should do blood tests to check your levels of cyclosporine or tacrolimus if you are taking these medicines while taking Noxafil or Noxafil PowderMix. Tell your healthcare provider right away if you have swelling in your arm or leg or shortness of breath.
- problems with the electrical system of your heart (arrhythmias and QTc prolongation). Certain medicines used to treat fungus called azoles, including posaconazole, the active ingredient in Noxafil and Noxafil PowderMix, may cause heart rhythm problems. People who have certain heart problems or who take certain medicines have a higher chance for this problem. Tell your healthcare provider right away if your heartbeat becomes fast or irregular.
- changes in body salt (electrolytes) levels in your blood. Your healthcare provider should check your electrolytes while you are taking Noxafil or Noxafil PowderMix.
- new or worsening high blood pressure and low potassium levels in your blood (pseudoaldosteronism). Your healthcare provider should check your blood pressure and potassium levels.
- liver problems. Some people who also have other serious medical problems may have severe liver problems that may lead to death, especially if you take certain doses of Noxafil or Noxafil PowderMix. Your healthcare provider should do blood tests to check your liver while you are taking Noxafil or Noxafil PowderMix. Call your healthcare provider right away if you have any of the following symptoms of liver problems:
  - itchy skin
  - nausea or vomiting
  - yellowing of your eyes or skin
  - feeling very tired
  - flu-like symptoms

- increased amounts of midazolam in your blood. If you take Noxafil or Noxafil PowderMix with midazolam, Noxafil or Noxafil PowderMix increases the amount of midazolam in your blood. This can make your sleepiness last longer. Your healthcare provider should check you closely for side effects if you take midazolam with Noxafil or Noxafil PowderMix.

The most common side effects of Noxafil in adults include:

- diarrhea
- nausea
- fever
- vomiting

- headache
- coughing
- low potassium levels in the blood

The most common side effects of Noxafil injection and Noxafil PowderMix in children include:

- fever
- fever with low white blood cell count (febrile neutropenia)
- vomiting
- redness and sores of the lining of the mouth, lips, throat, stomach, and genitals (mucositis or stomatitis)

- itching
- high blood pressure
- low potassium levels in the blood

If you take Noxafil delayed-release tablets, Noxafil oral suspension, or Noxafil PowderMix for delayed-release oral suspension, tell your healthcare provider right away if you have diarrhea or vomiting.
Tell your healthcare provider if you have any side effect that bothers you or that does not go away.
These are not all the possible side effects of Noxafil or Noxafil PowderMix. For more information, ask your healthcare provider or pharmacist.
Call your doctor for medical advice about side effects. You may report side effects to FDA at 1-800-FDA-1088.

How should I store Noxafil or Noxafil PowderMix?

Noxafil injection

- Store Noxafil injection refrigerated between 36°F to 46°F (2°C to 8°C).

Noxafil delayed-release tablets

- Store Noxafil delayed-release tablets at room temperature between 68°F to 77°F (20°C to 25°C).

Noxafil oral suspension

- Store Noxafil oral suspension at room temperature between 68°F to 77°F (20°C to 25°C).
- Do not freeze Noxafil oral suspension.

Noxafil PowderMix for delayed-release oral suspension

- Store the entire kit at room temperature between 68°F to 77°F (20°C to 25°C) in a clean, dry place.
- Do not open the foil packet until ready for use.

Safely throw away medicine that is out of date or no longer needed.

Keep Noxafil and Noxafil PowderMix and all medicines out of the reach of children.

General information about the safe and effective use of Noxafil and Noxafil PowderMix.

Medicines are sometimes prescribed for purposes other than those listed in a Patient Information leaflet. Do not use Noxafil or Noxafil PowderMix for a condition for which it was not prescribed. Do not give Noxafil or Noxafil PowderMix to other people, even if they have the same symptoms that you have. It may harm them. You can ask your pharmacist or healthcare provider for information about Noxafil or Noxafil PowderMix that is written for health professionals.

What are the ingredients in Noxafil and Noxafil PowderMix?
Active ingredient: posaconazole
Inactive ingredients:
Noxafil injection: Betadex Sulfobutyl Ether Sodium (SBECD), edetate sodium, hydrochloric acid, sodium hydroxide, and water for injection.
Noxafil delayed-release tablets: croscarmellose sodium, hydroxypropylcellulose, hypromellose acetate succinate, iron oxide yellow, Macrogol/PEG 3350, magnesium stearate, microcrystalline cellulose, polyvinyl alcohol partially hydrolyzed, silicon dioxide, talc, and titanium dioxide.
Noxafil oral suspension: artificial cherry flavor, citric acid monohydrate, glycerin, liquid glucose, polysorbate 80, purified water, simethicone, sodium benzoate, sodium citrate dihydrate, titanium dioxide, and xanthan gum.
Noxafil PowderMix for delayed-release oral suspension: hypromellose acetate succinate. The mixing liquid contains: anhydrous citric acid, antifoam Af emulsion, berry citrus sweet flavor, carboxymethylcellulose sodium, carrageenan calcium sulfate trisodium phosphate, glycerin, methylparaben, microcrystalline cellulose, potassium sorbate, propylparaben, purified water, sodium citrate, sodium phosphate monobasic monohydrate, sodium saccharin, sorbitol solution, and xanthan gum.

Manuf. for: Merck Sharp & Dohme LLC
Rahway, NJ 07065, USA
For patent information: www.msd.com/research/patent
The trademarks depicted in this piece are owned by their respective companies.
Copyright © 2006-2026 Merck & Co., Inc., Rahway, NJ, USA, and its affiliates.
All rights reserved.
usppi-mk5592-mf-2601r024
For more information, go to www.noxafil.com or call 1-800-672-6372.

This Patient Information has been approved by the U.S. Food and Drug Administration. Revised: 1/2026

INSTRUCTIONS FOR USE

Important: Read This Booklet First
Noxafil PowderMix (posaconazole)
for delayed-release oral suspension
Instructions for Use
for caregivers and healthcare providers of toddlers and children

Before You Start

- Before you start, be sure that you read and understand
  all of these instructions. They may be different than those
  for medicines that you have used in the past.
- It is important that you make all
  measurements very carefully.
- Before you give Noxafil PowderMix,
  check all 3 expiration dates. The
  expiration date is printed on the box,
  the Noxafil PowderMix packets, and the
  mixing liquid.
- Do not open the Noxafil PowderMix
  packets until you are ready to mix the
  dose.
- Give Noxafil PowderMix with food.

Note: Put your child in a safe place. You will need both hands to prepare Noxafil PowderMix. Wash your hands with soap and water before preparing Noxafil PowderMix.

Before You Start

- The amount of Noxafil PowderMix you give depends on your child’s weight. Your healthcare provider will tell you the right dose to give your child. Be sure to keep your healthcare provider’s appointments so you get new dosing information as your child grows.
- This booklet tells you how to:
  - Make the Noxafil PowderMix into a liquid form.
  - Measure the right dose using the included notched-tip
    oral syringe. Only use the notched-tip syringes supplied
    with the kit. Do not use other oral syringes.
  - Give the Noxafil PowderMix to your child.
  - Clean up.

Note before adding Noxafil PowderMix: Make sure you and your child are ready! If you do not use Noxafil PowderMix within 1 hour, you will need to throw it away and start over.

Note: If you have any questions, call your healthcare provider.

Kit Contents

- Prescription
  (on Noxafil
  PowderMix box)

- 2 mixing cups

- Instructions for Use (this
  booklet)

- 8 packets
  of Noxafil PowderMix

- Package insert

- Bottle adapter

- 4 syringes (shown below)

- Bottle of Mixing Liquid
  for use with Noxafil
  PowderMix

2 blue (10 mL) syringes

2 green (3 mL) syringes

The kit has an extra cup and set of syringes in case one is lost or damaged.
Do not use any damaged cups or syringes.

Get to Know the Oral Syringes

- Before you prepare a dose, review
  the parts of the syringe and how to
  use them.
- If you have any questions about
  measuring with a syringe, call your
  healthcare provider.
- Make sure the plunger is pushed
  all the way into the barrel before
  you start to measure the dose.

- Look for the number on the measuring scale that matches
  the amount of mixing liquid or Noxafil PowderMix that
  you need.
- Be sure to follow the directions in this booklet to remove
  air bubbles from the syringe. Air bubbles can affect the
  amount of medicine that the child gets.

Step 1. Get the mixing liquid ready.

Important: Noxafil PowderMix needs to be prepared using the mixing liquid. Do not mix Noxafil PowderMix with milk, juice, or water.

When you use the mixing liquid for the first time:

- Open the bottle and remove the safety seal.
- Place the bottle adapter on top of the bottle with
  the small hole facing up.
- Push the bottle adapter all the way down.
- After it is in place, the bottle adapter stays in the bottle.
- Put the cap back on the bottle.

Step 2. Gather all your supplies and
put on a clean surface.

Note: Put your child in a safe place. You will need both hands to prepare Noxafil PowderMix. Wash your hands with soap and water before preparing Noxafil PowderMix.

1 mixing cup
(Using the tab
on the mixing
cup, pull open
the lid.)

1 packet of
Noxafil PowderMix
powder

Mixing liquid

2 syringes
(Have 1 of each
size ready, but
you may only use
1, depending on
the dose.)

Scissors
(not included
with kit:
use sharp
household
scissors or
kitchen scissors)

The Noxafil PowderMix box has a mixing cup holder inside to help tilt the cup when you are measuring the dose.

Step 3. Add Noxafil PowderMix to the
mixing cup.

Note before adding Noxafil PowderMix:
Make sure you and your child are ready! If you do not use Noxafil PowderMix within 1 hour, you will need to throw it away and start over.

- Take 1 packet of Noxafil
  PowderMix and shake the
  powder to the bottom of
  the packet.

- Cut open the packet of Noxafil
  PowderMix at the dotted line
  and add all of the Noxafil
  PowderMix to the mixing cup.
  Make sure the packet of Noxafil
  PowderMix is completely empty.

Step 4. Shake the mixing liquid bottle.

- Shake the mixing liquid well before each
  time you prepare Noxafil PowderMix.

Step 5. Fill the blue syringe with 9 mL of mixing liquid.

- Push the plunger of the
  blue syringe into the
  syringe barrel as far as
  it goes.
- Remove the cap from the bottle of
  mixing liquid.
- Push the notched tip of the syringe into the
  bottle adapter.
- With the syringe attached to the bottle, turn
  the bottle and syringe upside down. With
  your other hand, pull back the plunger to
  draw the mixing liquid back into the syringe.
- Stop when you get to the 9 mL line.
- Turn the bottle back over and remove the
  syringe to check your measurement.

Step 6. Check for air bubbles.

- Hold the syringe with
  notched tip up. Tap it
  with your finger to move
  any air bubbles up.
- Slowly push the plunger
  to make the air come out.

- Re-check the measurement
  of mixing liquid in the
  syringe. If it is less than
  9 mL, put the notched tip
  back into the mixing liquid
  and pull the plunger back
  until you get to the
  9 mL mark.

Step 7. Add the 9 mL of mixing liquid
to the Noxafil PowderMix.

- Add the 9 mL of mixing liquid to the Noxafil PowderMix
  in the mixing cup by pushing all the way down on the
  plunger.

Step 8. Mix the Noxafil PowderMix.

- Snap the lid of the mixing cup shut.
- Shake the mixing cup really hard for 45 seconds to mix the Noxafil PowderMix.

- Check to make sure the
  Noxafil PowderMix powder
  is mixed. If it is not mixed,
  shake the mixing cup some
  more. Noxafil PowderMix
  should look cloudy and free
  of clumps.

Step 9. Check your prescription label.

- Find the dose amount (look for the 'mL' written on the
  prescription label on the box from your healthcare provider).

Note: The dose may change each time you go to the healthcare provider, so make sure you have all the recent information. Be sure to go to all of your child's healthcare provider appointments so your child gets the right dose.

Step 10. Choose the syringe you need.

Note: Only use the syringes provided in the kit.

Choose the correct syringe for your child's dose:

For 1 mL
to 3 mL
Green

For 3 mL
to 10 mL
Blue

- Then find the mL mark on the syringe that matches your
  child's dose.

Step 11. Measure the Noxafil PowderMix.

- Push the plunger into the
  dosing syringe as far as
  it goes.
- Tilt the cup by hand or use
  the mixing cup holder inside
  the Noxafil PowderMix box.
- Put the notched tip of the
  dosing syringe into the
  lowest part of the cup with
  the Noxafil PowderMix and
  pull back the plunger.
- Stop when you get to the line
  showing the prescribed dose.

Important: You will not use all of the Noxafil PowderMix. There will be some left over in the mixing cup.

Step 12. Check for air bubbles.

- Be sure to follow the directions to
  remove air bubbles from the syringe.
  Air bubbles can affect the amount of
  medicine that the child gets.
- Hold the syringe with notched tip up.
  Tap it with your finger to move any
  air bubbles up. Check for air gaps in
  the tip of the syringe. Slowly push
  the plunger to make the air bubbles
  or air gaps come out.

- Re-check the measurement of
  Noxafil PowderMix in the
  syringe. If it is less than the
  prescribed dose, put the notched
  tip back into the mixing cup
  with the Noxafil PowderMix and
  pull the plunger back until you
  get to the right dose mark.

Step 13. Give the Noxafil PowderMix to
your child.

- Gently place the syringe
  inside your child’s mouth
  so that the notched tip
  touches one of his or
  her cheeks.
- Slowly push down on the plunger to give the dose of
  Noxafil PowderMix. It is important that your child takes
  all of the dose of Noxafil PowderMix (a little left in the
  syringe notched tip is ok).

Important:

- If your child does not take the whole dose or spits
  some of it out, call your healthcare provider to find out what to do.
- Only use the mixing liquid from the kit. Do not mix
  Noxafil PowderMix with milk, juice, or water.

Step 14. Clean the cup and syringes.

Note: Syringes and mixing cups should be reused. Do not throw away syringes and mixing cups provided until all the Noxafil PowderMix packets are used.

- Pour the leftover Noxafil PowderMix from the
  mixing cup into the trash.
  Do not pour it into the sink.
- Pull the plungers out of any syringes you used.
- Hand wash the syringes, plungers, and mixing
  cup with warm water and dish soap. Do not
  wash in the dishwasher.
- Rinse with water and air dry.
- Put everything in a clean, dry place.

Step 15. After all packets of Noxafil
PowderMix have been used.

- After you have used the last Noxafil PowderMix packet
  in this box, you will have leftover mixing liquid in the
  bottle. Throw away the leftover mixing liquid and all
  components of the kit.

How should I store Noxafil PowderMix?

- Store the entire kit at room temperature between 68°F to
  77°F (20°C to 25°C) in a clean, dry place.
- Keep the mixing liquid at room temperature.
- Do not open the Noxafil PowderMix packet until you are
  ready to mix a dose.

Keep NOXAFIL PowderMix and all medicines out of the reach of children.

For more information go to www.Noxafil.com or call
1-800-622-4477.

Distributed by:
Merck Sharp & Dohme LLC
Rahway, NJ 07065, USA

For patent information: www.msd.com/research/patent

Copyright © 2021-2022 Merck & Co., Inc., Rahway, NJ, USA, and its affiliates.
All rights reserved.

ifu-mk5592-2209r002

This Instructions for Use has been approved by the U.S. Food and
Drug Administration.

Revised: September 2022

PRINCIPAL DISPLAY PANEL - 105 mL Bottle Carton

NDC 0085-1328-01
105 mL

NOXAFIL®
(posaconazole)

Oral Suspension

200 mg/5 mL

Each mL contains: 40 mg posaconazole.

Attention: Noxafil Oral Suspension is
NOT substitutable with Noxafil
Delayed-Release Tablets or Noxafil PowderMix
for Delayed-Release Oral Suspension due to
differences in the dosing of each formulation.

SHAKE WELL BEFORE EACH USE.

Take with a meal, or a nutritional supplement,
or an acidic carbonated beverage.

Carton contains measured dosing spoon.

Rx only

PRINCIPAL DISPLAY PANEL - 60 Tablet Bottle Label

NDC 0085-4324-02

Noxafil®
(posaconazole)
delayed-release tablets

100 mg

Each tablet contains 100 mg posaconazole.

Attention: Noxafil Oral Suspension and Delayed-
Release Tablets are NOT substitutable due to
differences in the dosing of each formulation.

Rx only

60 Tablets

PRINCIPAL DISPLAY PANEL - 16.7 mL Vial Carton

NDC 0085-4331-01

Noxafil®
(posaconazole)
Injection

300 mg/16.7 mL
(18 mg/mL)

For Intravenous Use Only

Requires further dilution prior to infusion.

Rx only
Sterile Single-Dose Vial
Discard Unused Portion

PRINCIPAL DISPLAY PANEL - 300 mg Carton

NDC 0085-2224-02

Noxafil® PowderMix
(posaconazole) for
Delayed-Release Oral Suspension

300 mg

For Pediatric Use
For Oral Administration Only

Each packet contains 300 mg posaconazole.

Attention: Noxafil PowderMix for Delayed-Release Oral Suspension is NOT
substitutable with Noxafil Oral Suspension due to differences in the
dosing of each formulation.

Use only the notched-tip syringes and mixing liquid provided with this kit.

Rx only
8 packets

Multi-Dose Kit A
Additional notched-tip syringes are provided in
Package B with this kit.
DIRECTIONS FOR USE:
See instructions for use booklet and prescribing
information for additional information.